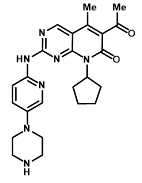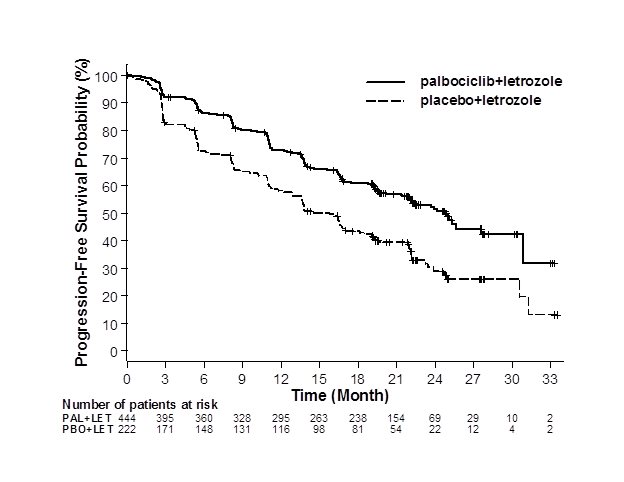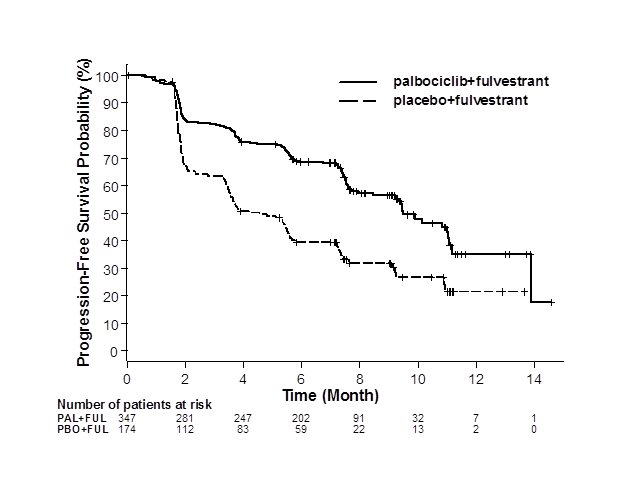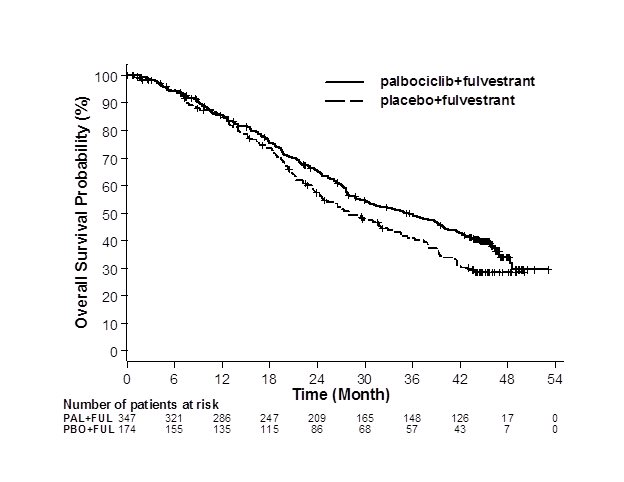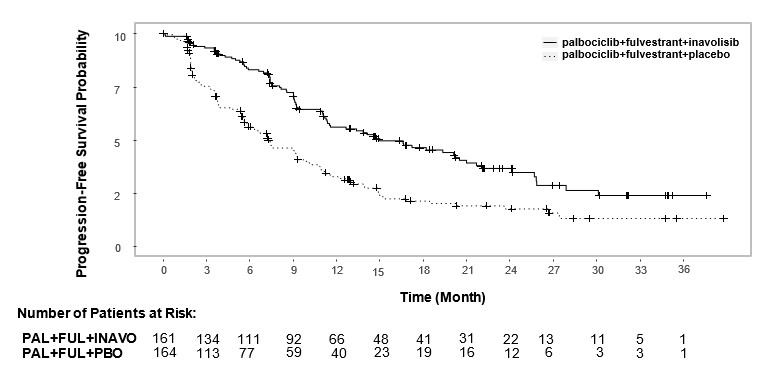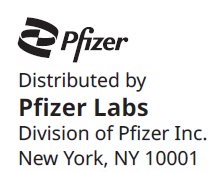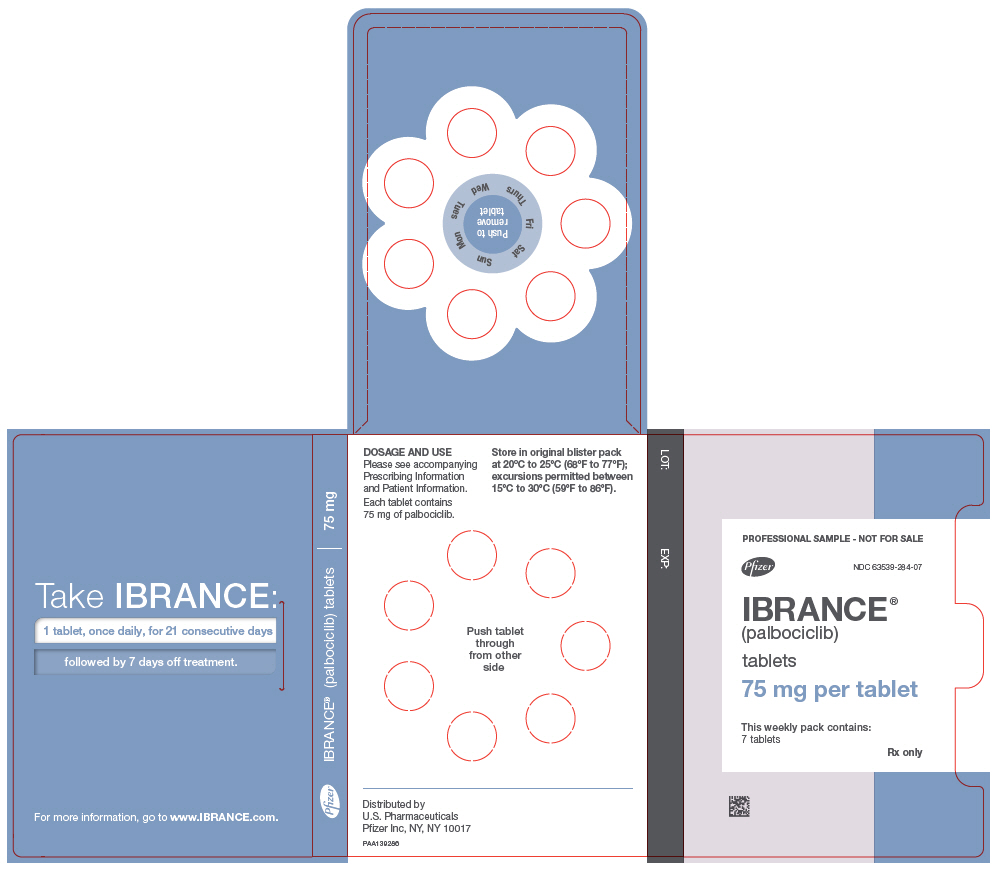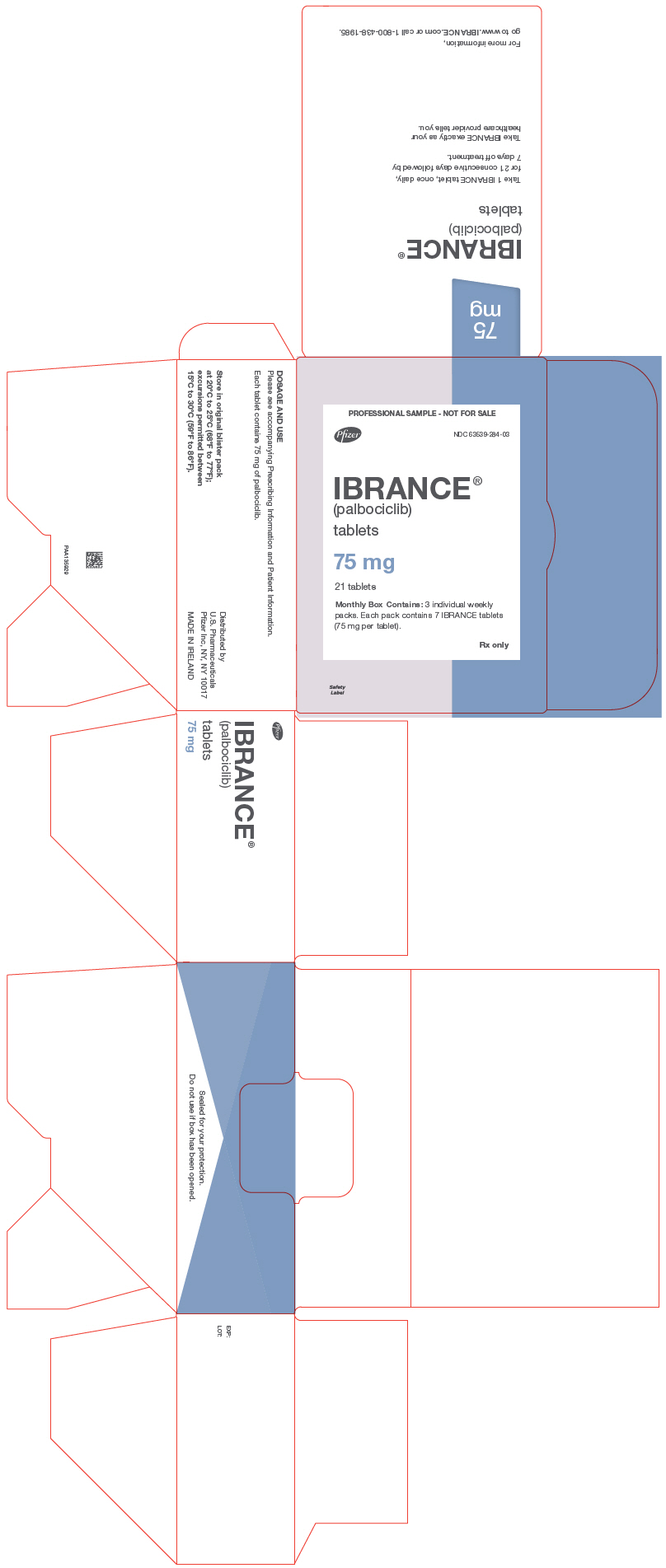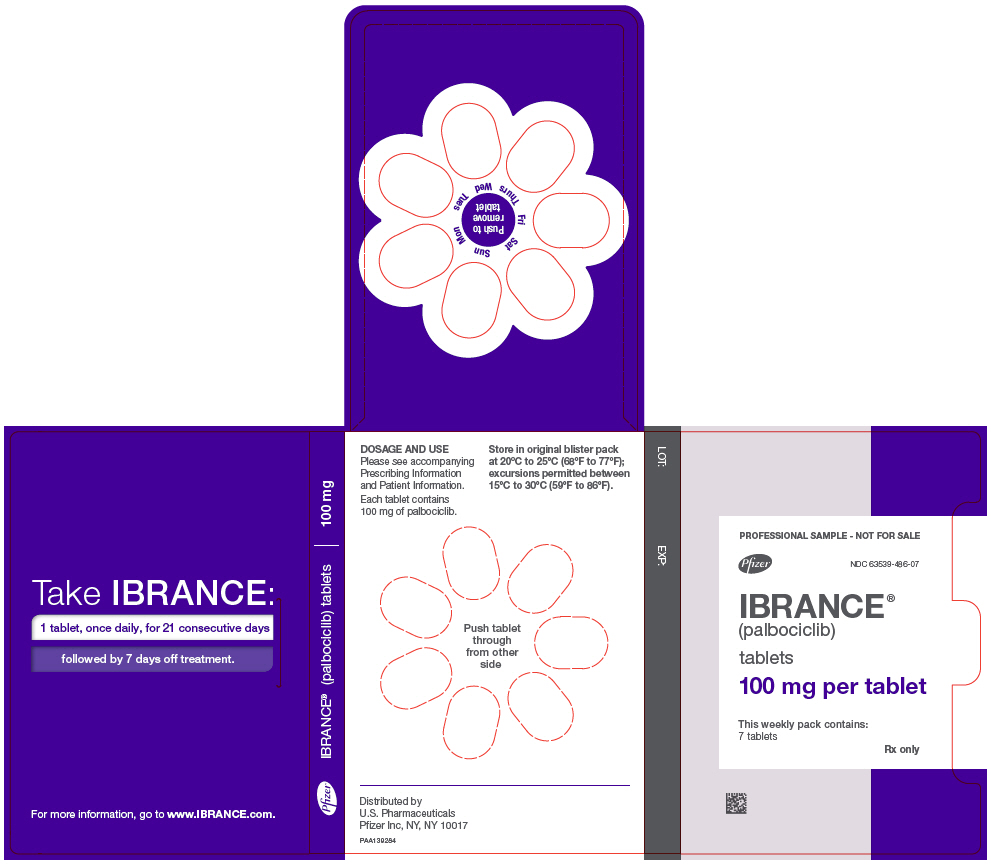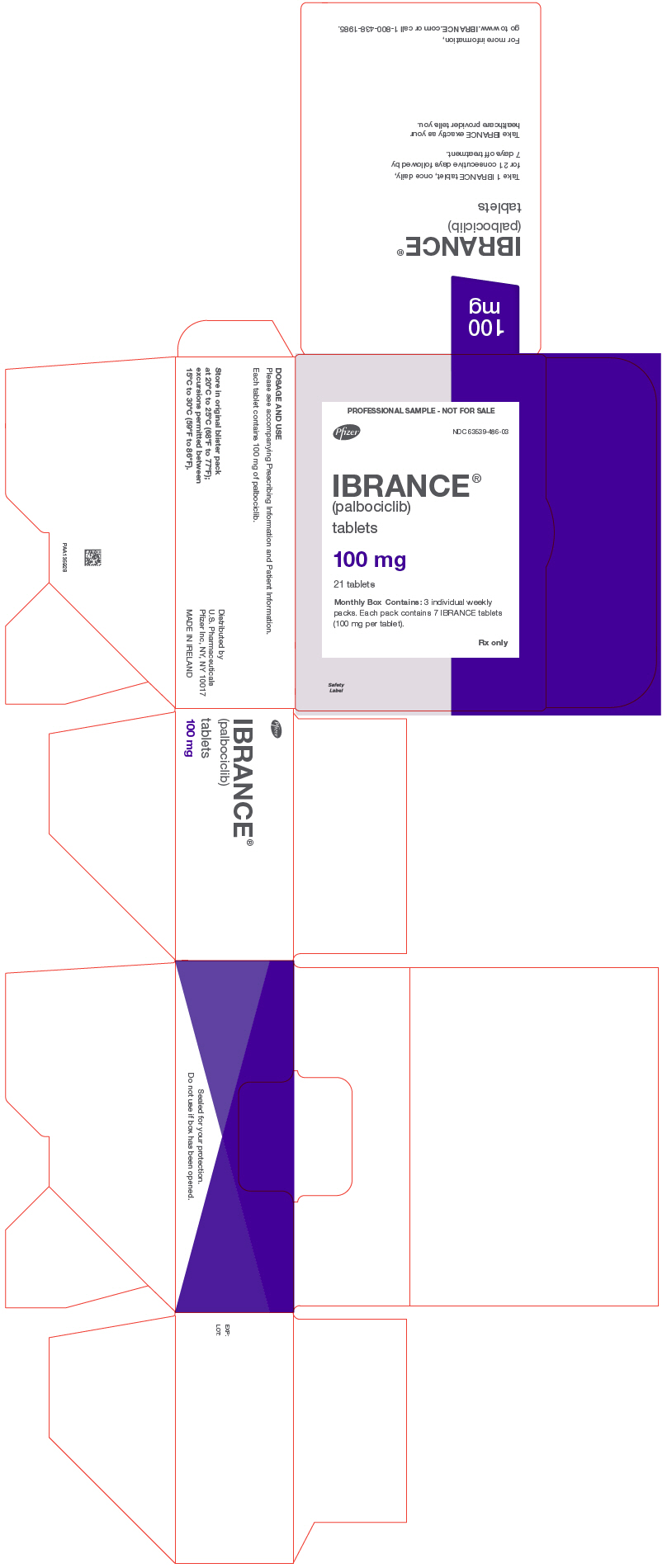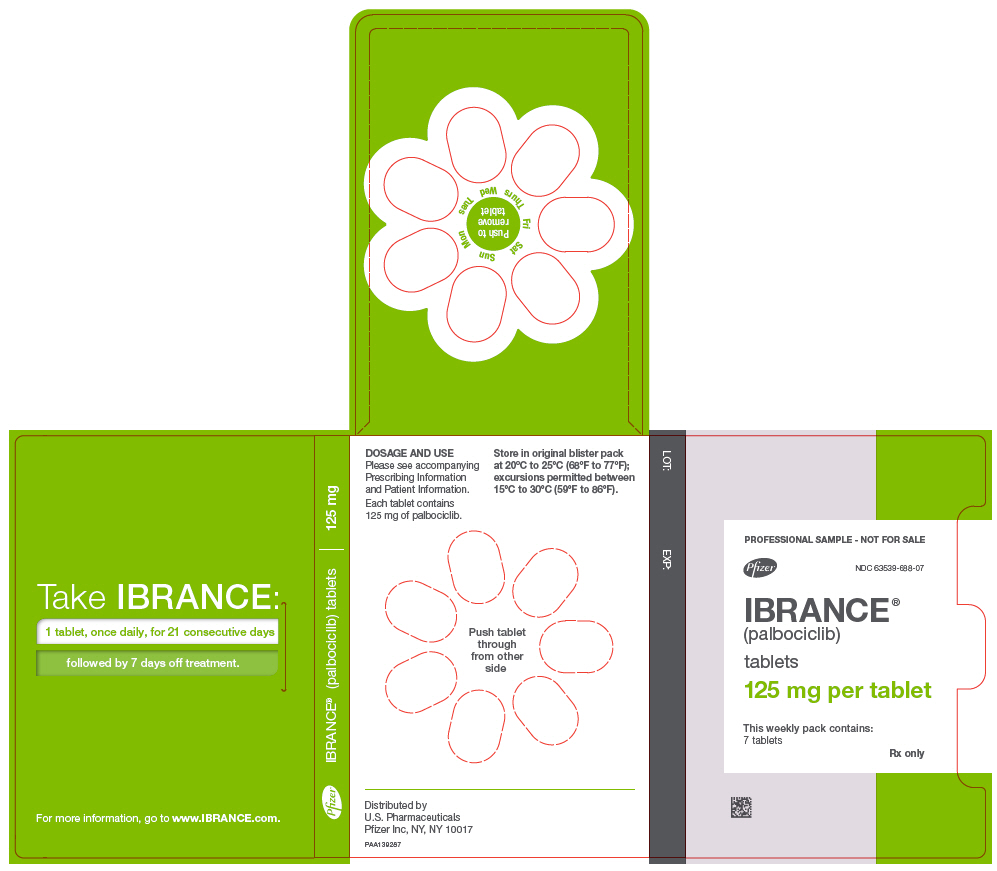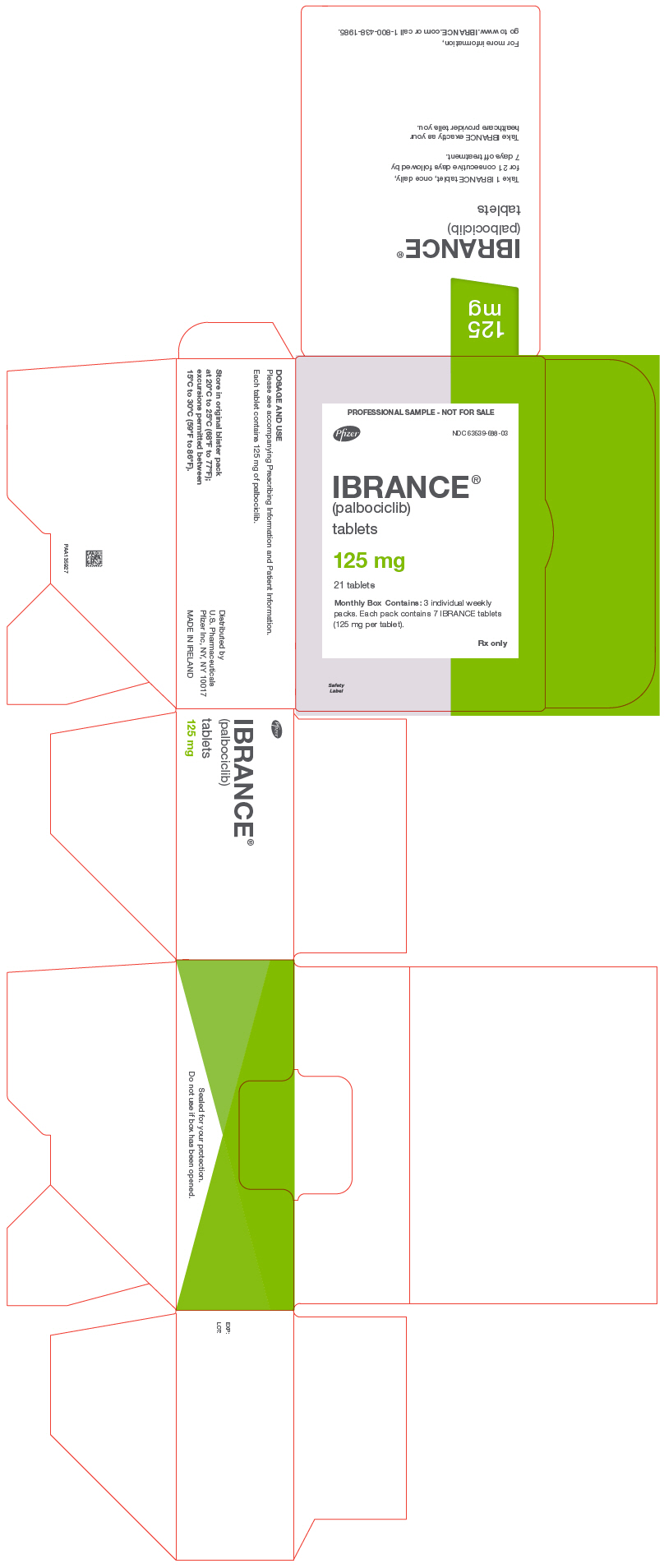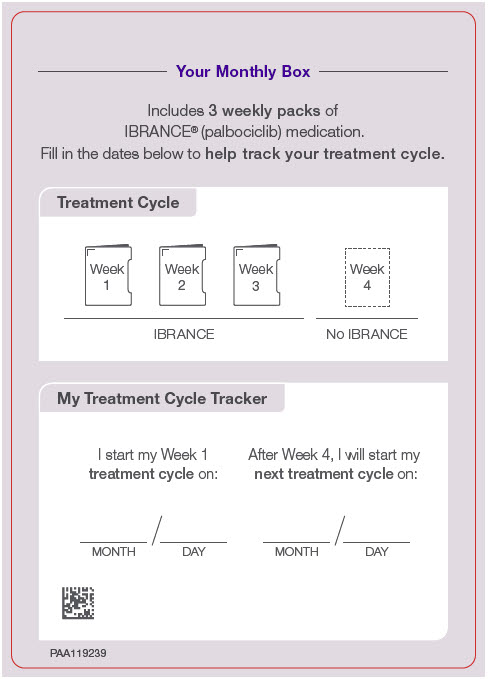 DRUG LABEL: Ibrance
NDC: 63539-284 | Form: TABLET, FILM COATED
Manufacturer: U.S. Pharmaceuticals
Category: prescription | Type: HUMAN PRESCRIPTION DRUG LABEL
Date: 20251002

ACTIVE INGREDIENTS: PALBOCICLIB 75 mg/1 1
INACTIVE INGREDIENTS: MICROCRYSTALLINE CELLULOSE; SILICON DIOXIDE; MAGNESIUM STEARATE; FERRIC OXIDE RED; TITANIUM DIOXIDE; CROSPOVIDONE, UNSPECIFIED; SUCCINIC ACID; HYPROMELLOSE 2910 (6 MPA.S); TRIACETIN; FD&C BLUE NO. 2

HIGHLIGHTS OF PRESCRIBING INFORMATION

These highlights do not include all the information needed to use IBRANCE safely and effectively. See full prescribing information for IBRANCE.
IBRANCE® (palbociclib) tablets, for oral use
Initial U.S. Approval: 2015

RECENT MAJOR CHANGES

Indications and Usage (1) | 4/2025
Dosage and Administration (2.1, 2.2) | 4/2025

1 INDICATIONS AND USAGE

IBRANCE is a kinase inhibitor indicated:

- for the treatment of adult patients with hormone receptor (HR)-positive, human epidermal growth factor receptor 2 (HER2)-negative advanced or metastatic breast cancer in combination with:
  - an aromatase inhibitor as initial endocrine-based therapy (1); or
  - fulvestrant in patients with disease progression following endocrine therapy. (1)
- in combination with inavolisib and fulvestrant for the treatment of adult patients with endocrine-resistant, PIK3CA-mutated, HR-positive, HER2-negative, locally advanced or metastatic breast cancer, as detected by an FDA-approved test, following recurrence on or after completing adjuvant endocrine therapy. (1)

2 DOSAGE AND ADMINISTRATION

IBRANCE tablets are taken orally with or without food in combination with an aromatase inhibitor, fulvestrant, or inavolisib and fulvestrant. (2)

- Recommended starting dose: 125 mg once daily taken with or without food for 21 days followed by 7 days off treatment. (2.1)
- Dosing interruption and/or dose reductions are recommended based on individual safety and tolerability. (2.2)

3 DOSAGE FORMS AND STRENGTHS

Tablets: 125 mg, 100 mg, and 75 mg. (3)

4 CONTRAINDICATIONS

None. (4)

5 WARNINGS AND PRECAUTIONS

- Neutropenia: Monitor complete blood count prior to start of IBRANCE therapy and at the beginning of each cycle, as well as on Day 15 of the first 2 cycles, and as clinically indicated. (2.2, 5.1)
- Interstitial Lung Disease (ILD)/Pneumonitis: Severe and fatal cases of ILD/pneumonitis have been reported. Monitor for pulmonary symptoms of ILD/pneumonitis. Interrupt IBRANCE immediately in patients with suspected ILD/pneumonitis. Permanently discontinue IBRANCE if severe ILD/pneumonitis occurs. (5.2)
- Embryo-Fetal Toxicity: IBRANCE can cause fetal harm. Advise patients of potential risk to a fetus and to use effective contraception. (5.3, 8.1, 8.3)

6 ADVERSE REACTIONS

Most common adverse reactions (incidence ≥20%) in combination with either letrozole or fulvestrant, including laboratory abnormalities, were white blood cell count decreased, neutrophils decreased, blood creatinine increased, hemoglobin decreased, platelets decreased, infections, aspartate aminotransferase increased, alanine aminotransferase increased, fatigue, nausea, stomatitis, diarrhea, and alopecia. (6.1)
The most common adverse reactions (incidence ≥20%) in combination with inavolisib and fulvestrant, including laboratory abnormalities, were neutrophils decreased, hemoglobin decreased, fasting glucose increased, platelets decreased, lymphocytes decreased, stomatitis, diarrhea, calcium decreased, fatigue, potassium decreased, creatinine increased, alanine aminotransferase (ALT) increased, nausea, sodium decreased, magnesium decreased, rash, decreased appetite, COVID-19 infection, and headache. (6.1)

To report SUSPECTED ADVERSE REACTIONS, contact Pfizer Inc at 1-800-438-1985 or FDA at 1-800-FDA-1088 or www.fda.gov/medwatch.

7 DRUG INTERACTIONS

- CYP3A Inhibitors: Avoid concurrent use of IBRANCE with strong CYP3A inhibitors. If the strong inhibitor cannot be avoided, reduce the IBRANCE dose. (2.2, 7.1)
- CYP3A Inducers: Avoid concurrent use of IBRANCE with strong CYP3A inducers. (7.2)
- CYP3A Substrates: The dose of sensitive CYP3A4 substrates with narrow therapeutic indices may need to be reduced when given concurrently with IBRANCE. (7.3)

8 USE IN SPECIFIC POPULATIONS

- Lactation: Advise not to breastfeed. (8.2)

FULL PRESCRIBING INFORMATION

1 INDICATIONS AND USAGE

IBRANCE is indicated for the treatment of adult patients with hormone receptor (HR)-positive, human epidermal growth factor receptor 2 (HER2)-negative advanced or metastatic breast cancer in combination with:

- an aromatase inhibitor as initial endocrine-based therapy; or
- fulvestrant in patients with disease progression following endocrine therapy.

IBRANCE is indicated in combination with inavolisib and fulvestrant for the treatment of adult patients with endocrine-resistant, PIK3CA-mutated, HR-positive, HER2-negative, locally advanced or metastatic breast cancer, as detected by an FDA-approved test, following recurrence on or after completing adjuvant endocrine therapy.

2 DOSAGE AND ADMINISTRATION

2.1 Recommended Dose and Schedule

The recommended dose of IBRANCE is a 125 mg tablet taken orally once daily for 21 consecutive days followed by 7 days off treatment to comprise a complete cycle of 28 days. IBRANCE tablet may be taken with or without food [see Clinical Pharmacology (12.3)].

Administer the recommended dose of an aromatase inhibitor when given with IBRANCE. Please refer to the Full Prescribing Information for the aromatase inhibitor being used.

When given with IBRANCE, the recommended dose of fulvestrant is 500 mg administered on Days 1, 15, 29, and once monthly thereafter. Please refer to the Full Prescribing Information of fulvestrant.

Refer to the Full Prescribing Information for inavolisib and fulvestrant for dosing information.

Advise patients to take their dose of IBRANCE at approximately the same time each day.

If the patient vomits or misses a dose, an additional dose should not be taken. The next prescribed dose should be taken at the usual time. IBRANCE tablets should be swallowed whole (do not chew, crush, or split them prior to swallowing). Tablets should not be ingested if they are broken, cracked, or otherwise not intact.

Pre/perimenopausal women treated with the combination IBRANCE plus an aromatase inhibitor or fulvestrant therapy or IBRANCE plus inavolisib and fulvestrant should also be treated with luteinizing hormone-releasing hormone (LHRH) agonists according to current clinical practice standards.

For men treated with combination IBRANCE plus aromatase inhibitor or IBRANCE plus inavolisib and fulvestrant therapy, consider treatment with an LHRH agonist according to current clinical practice standards.

2.2 Dose Modification

The recommended dose modifications for adverse reactions are listed in Tables 1, 2, and 3.

Table 1. Recommended Dose Modification for Adverse Reactions
Dose Level | Dose
Recommended starting dose | 125 mg/day
First dose reduction | 100 mg/day
Second dose reduction | 75 mg/day [If further dose reduction below 75 mg/day is required, discontinue.]

Table 2. Dose Modification and Management – Hematologic Toxicities [Table applies to all hematologic adverse reactions except lymphopenia (unless associated with clinical events, e.g., opportunistic infections).]
Monitor complete blood counts prior to the start of IBRANCE therapy and at the beginning of each cycle, as well as on Day 15 of the first 2 cycles, and as clinically indicated.
For patients who experience a maximum of Grade 1 or 2 neutropenia in the first 6 cycles, monitor complete blood counts for subsequent cycles every 3 months, prior to the beginning of a cycle and as clinically indicated.
CTCAE Grade | Dose Modifications
Grade 1 or 2 | No dose adjustment is required.
Grade 3 | Day 1 of cycle: Withhold IBRANCE, repeat complete blood count monitoring within 1 week. When recovered to Grade ≤2, start the next cycle at the same dose. Day 15 of first 2 cycles: If Grade 3 on Day 15, continue IBRANCE at current dose to complete cycle and repeat complete blood count on Day 22. If Grade 4 on Day 22, see Grade 4 dose modification guidelines below. Consider dose reduction in cases of prolonged (>1 week) recovery from Grade 3 neutropenia or recurrent Grade 3 neutropenia on Day 1 of subsequent cycles.
Grade 3 neutropenia [Absolute neutrophil count (ANC): Grade 1: ANC < LLN – 1500/mm^3; Grade 2: ANC 1000 – <1500/mm^3; Grade 3: ANC 500 – <1000/mm^3; Grade 4: ANC <500/mm^3.] with fever ≥38.5 °C and/or infection | At any time: Withhold IBRANCE until recovery to Grade ≤2. Resume at the next lower dose.
Grade 4 | At any time: Withhold IBRANCE until recovery to Grade ≤2. Resume at the next lower dose.
Grading according to CTCAE 4.0.
CTCAE=Common Terminology Criteria for Adverse Events; LLN=lower limit of normal.

Table 3. Dose Modification and Management – Non-Hematologic Toxicities
CTCAE Grade | Dose Modifications
Grade 1 or 2 | No dose adjustment is required.
Grade ≥3 non-hematologic toxicity (if persisting despite optimal medical treatment) | Withhold until symptoms resolve to:; - Grade ≤1; - Grade ≤2 (if not considered a safety risk for the patient); Resume at the next lower dose.
Grading according to CTCAE 4.0.
CTCAE=Common Terminology Criteria for Adverse Events.

Permanently discontinue IBRANCE in patients with severe interstitial lung disease (ILD)/pneumonitis.

Refer to the Full Prescribing Information for coadministered endocrine therapy and/or inavolisib dose adjustment guidelines in the event of toxicity and other relevant safety information or contraindications.

Dose Modifications for Use With Strong CYP3A Inhibitors

Avoid concomitant use of strong CYP3A inhibitors and consider an alternative concomitant medication with no or minimal CYP3A inhibition. If patients must be coadministered a strong CYP3A inhibitor, reduce the IBRANCE dose to 75 mg once daily. If the strong inhibitor is discontinued, increase the IBRANCE dose (after 3 to 5 half-lives of the inhibitor) to the dose used prior to the initiation of the strong CYP3A inhibitor [see Drug Interactions (7.1) and Clinical Pharmacology (12.3)].

Dose Modifications for Hepatic Impairment

No dose adjustment is required for patients with mild or moderate hepatic impairment (Child-Pugh classes A and B). For patients with severe hepatic impairment (Child-Pugh class C), the recommended dose of IBRANCE is 75 mg once daily for 21 consecutive days followed by 7 days off treatment to comprise a complete cycle of 28 days [see Use in Specific Populations (8.6) and Clinical Pharmacology (12.3)].

3 DOSAGE FORMS AND STRENGTHS

125 mg tablets: Oval, light purple, film-coated tablets debossed with "Pfizer" on one side and "PBC 125" on the other side.

100 mg tablets: Oval, green, film-coated tablets debossed with "Pfizer" on one side and "PBC 100" on the other side.

75 mg tablets: Round, light purple, film-coated tablets debossed with "Pfizer" on one side and "PBC 75" on the other side.

4 CONTRAINDICATIONS

None.

5 WARNINGS AND PRECAUTIONS

5.1 Neutropenia

Neutropenia was the most frequently reported adverse reaction in PALOMA-2 with an incidence of 80% and PALOMA-3 with an incidence of 83%. A Grade ≥3 decrease in neutrophil counts was reported in 66% of patients receiving IBRANCE plus letrozole in PALOMA-2 and 66% of patients receiving IBRANCE plus fulvestrant in PALOMA-3. In PALOMA-2 and PALOMA-3, the median time to first episode of any grade neutropenia was 15 days and the median duration of Grade ≥3 neutropenia was 7 days [see Adverse Reactions (6.1)].

Monitor complete blood counts prior to starting IBRANCE therapy and at the beginning of each cycle, as well as on Day 15 of the first 2 cycles, and as clinically indicated. Dose interruption, dose reduction, or delay in starting treatment cycles is recommended for patients who develop Grade 3 or 4 neutropenia [see Dosage and Administration (2.2)].

Febrile neutropenia has been reported in 1.8% of patients exposed to IBRANCE across PALOMA-2 and PALOMA-3. One death due to neutropenic sepsis was observed in PALOMA-3. Physicians should inform patients to promptly report any episodes of fever [see Patient Counseling Information (17)].

5.2 Interstitial Lung Disease (ILD)/Pneumonitis

Severe, life-threatening, or fatal interstitial lung disease (ILD) and/or pneumonitis can occur in patients treated with cyclin-dependent kinase 4/6 (CDK4/6) inhibitors, including IBRANCE when taken in combination with endocrine therapy.

Across clinical trials (PALOMA-1, PALOMA-2, PALOMA-3), 1% of IBRANCE-treated patients had ILD/pneumonitis of any grade, 0.1% had Grade 3 or 4 and no fatal cases were reported. Additional cases of ILD/pneumonitis have been observed in the postmarketing setting, with fatalities reported [see Adverse Reactions (6.2)].

Monitor patients for pulmonary symptoms indicative of ILD/pneumonitis (e.g. hypoxia, cough, dyspnea). In patients who have new or worsening respiratory symptoms and are suspected to have developed pneumonitis, interrupt IBRANCE immediately and evaluate the patient. Permanently discontinue IBRANCE in patients with severe ILD or pneumonitis [see Dosage and Administration (2.2)].

5.3 Embryo-Fetal Toxicity

Based on findings from animal studies and its mechanism of action, IBRANCE can cause fetal harm when administered to a pregnant woman. In animal reproduction studies, administration of palbociclib to pregnant rats and rabbits during organogenesis resulted in embryo-fetal toxicity at maternal exposures that were ≥4 times the human clinical exposure based on area under the curve (AUC). Advise pregnant women of the potential risk to a fetus. Advise females of reproductive potential to use effective contraception during treatment with IBRANCE and for at least 3 weeks after the last dose [see Use in Specific Populations (8.1 and 8.3) and Clinical Pharmacology (12.1)].

6 ADVERSE REACTIONS

The following clinically significant adverse reactions are described elsewhere in the labeling:

- Neutropenia [see Warnings and Precautions (5.1)]
- ILD/Pneumonitis [see Warnings and Precautions (5.2)]

6.1 Clinical Studies Experience

Because clinical trials are conducted under widely varying conditions, adverse reaction rates observed in the clinical trials of a drug cannot be directly compared to rates in the clinical trials of another drug and may not reflect the rates observed in practice.

PALOMA-2: IBRANCE plus Letrozole

Patients with estrogen receptor (ER)-positive, HER2-negative advanced or metastatic breast cancer for initial endocrine-based therapy

The safety of IBRANCE (125 mg/day) plus letrozole (2.5 mg/day) versus placebo plus letrozole was evaluated in PALOMA-2. The data described below reflect exposure to IBRANCE in 444 out of 666 patients with ER-positive, HER2-negative advanced breast cancer who received at least 1 dose of IBRANCE plus letrozole in PALOMA-2. The median duration of treatment for IBRANCE plus letrozole was 19.8 months while the median duration of treatment for placebo plus letrozole arm was 13.8 months.

Dose reductions due to an adverse reaction of any grade occurred in 36% of patients receiving IBRANCE plus letrozole. No dose reduction was allowed for letrozole in PALOMA-2.

Permanent discontinuation associated with an adverse reaction occurred in 43 of 444 (10%) patients receiving IBRANCE plus letrozole and in 13 of 222 (6%) patients receiving placebo plus letrozole. Adverse reactions leading to permanent discontinuation for patients receiving IBRANCE plus letrozole included neutropenia (1.1%) and alanine aminotransferase increase (0.7%).

The most common adverse reactions (≥10%) of any grade reported in patients in the IBRANCE plus letrozole arm by descending frequency were neutropenia, infections, leukopenia, fatigue, nausea, alopecia, stomatitis, diarrhea, anemia, rash, asthenia, thrombocytopenia, vomiting, decreased appetite, dry skin, pyrexia, and dysgeusia.

The most frequently reported Grade ≥3 adverse reactions (≥5%) in patients receiving IBRANCE plus letrozole by descending frequency were neutropenia, leukopenia, infections, and anemia.

Adverse reactions (≥10%) reported in patients who received IBRANCE plus letrozole or placebo plus letrozole in PALOMA-2 are listed in Table 4.

Table 4. Adverse Reactions (≥10%) in PALOMA-2
 | IBRANCE plus Letrozole (N=444) |  |  | Placebo plus Letrozole (N=222)
Adverse Reaction | All Grades % | Grade 3 % | Grade 4 % | All Grades % | Grade 3 % | Grade 4 %
Infections and infestations
Infections [Infections includes all reported preferred terms (PTs) that are part of the System Organ Class Infections and infestations.] | 60 [Most common infections (≥1%) include: nasopharyngitis, upper respiratory tract infection, urinary tract infection, oral herpes, sinusitis, rhinitis, bronchitis, influenza, pneumonia, gastroenteritis, conjunctivitis, herpes zoster, pharyngitis, cellulitis, cystitis, lower respiratory tract infection, tooth infection, gingivitis, skin infection, gastroenteritis viral, respiratory tract infection, respiratory tract infection viral, and folliculitis.] | 6 | 1 | 42 | 3 | 0
Blood and lymphatic system disorders
Neutropenia | 80 | 56 | 10 | 6 | 1 | 1
Leukopenia | 39 | 24 | 1 | 2 | 0 | 0
Anemia | 24 | 5 | <1 | 9 | 2 | 0
Thrombocytopenia | 16 | 1 | <1 | 1 | 0 | 0
Metabolism and nutrition disorders
Decreased appetite | 15 | 1 | 0 | 9 | 0 | 0
Nervous system disorders
Dysgeusia | 10 | 0 | 0 | 5 | 0 | 0
Gastrointestinal disorders
Stomatitis [Stomatitis includes: aphthous stomatitis, cheilitis, glossitis, glossodynia, mouth ulceration, mucosal inflammation, oral pain, oral discomfort, oropharyngeal pain, and stomatitis.] | 30 | 1 | 0 | 14 | 0 | 0
Nausea | 35 | <1 | 0 | 26 | 2 | 0
Diarrhea | 26 | 1 | 0 | 19 | 1 | 0
Vomiting | 16 | 1 | 0 | 17 | 1 | 0
Skin and subcutaneous tissue disorders
Alopecia | 33 [Grade 1 events – 30%; Grade 2 events – 3%.] | N/A | N/A | 16 [Grade 1 events – 15%; Grade 2 events – 1%.] | N/A | N/A
Rash [Rash includes the following PTs: rash, rash maculo-papular, rash pruritic, rash erythematous, rash papular, dermatitis, dermatitis acneiform, and toxic skin eruption.] | 18 | 1 | 0 | 12 | 1 | 0
Dry skin | 12 | 0 | 0 | 6 | 0 | 0
General disorders and administration site conditions
Fatigue | 37 | 2 | 0 | 28 | 1 | 0
Asthenia | 17 | 2 | 0 | 12 | 0 | 0
Pyrexia | 12 | 0 | 0 | 9 | 0 | 0
Grading according to CTCAE 4.0.
CTCAE=Common Terminology Criteria for Adverse Events; N=number of patients; N/A=not applicable;

Clinically relevant adverse reactions in <10% of patients who received IBRANCE plus letrozole in PALOMA-2 included epistaxis (9%), lacrimation increased (6%), dry eye (4.1%), vision blurred (3.6%), and febrile neutropenia (2.5%).

Table 5. Laboratory Abnormalities in PALOMA-2
 | IBRANCE plus Letrozole (N=444) |  |  | Placebo plus Letrozole (N=222)
Laboratory Abnormality | All Grades % | Grade 3 % | Grade 4 % | All Grades % | Grade 3 % | Grade 4 %
WBC decreased | 97 | 35 | 1 | 25 | 1 | 0
Blood creatinine increased | 96 | 2 | <1 | 91 | 0 | 0
Neutrophils decreased | 95 | 56 | 12 | 20 | 1 | 1
Hemoglobin decreased | 78 | 6 | 0 | 42 | 2 | 0
Platelets decreased | 63 | 1 | 1 | 14 | 0 | 0
Aspartate aminotransferase increased | 52 | 3 | 0 | 34 | 1 | 0
Alanine aminotransferase increased | 43 | 2 | <1 | 30 | 0 | 0
N=number of patients; WBC=white blood cells.

PALOMA-3: IBRANCE plus Fulvestrant

Patients with HR-positive, HER2-negative advanced or metastatic breast cancer who have had disease progression on or after prior adjuvant or metastatic endocrine therapy

The safety of IBRANCE (125 mg/day) plus fulvestrant (500 mg) versus placebo plus fulvestrant was evaluated in PALOMA-3. The data described below reflect exposure to IBRANCE in 345 out of 517 patients with HR-positive, HER2-negative advanced or metastatic breast cancer who received at least 1 dose of IBRANCE plus fulvestrant in PALOMA-3. The median duration of treatment for IBRANCE plus fulvestrant was 10.8 months while the median duration of treatment for placebo plus fulvestrant arm was 4.8 months.

Dose reductions due to an adverse reaction of any grade occurred in 36% of patients receiving IBRANCE plus fulvestrant. No dose reduction was allowed for fulvestrant in PALOMA-3.

Permanent discontinuation associated with an adverse reaction occurred in 19 of 345 (6%) patients receiving IBRANCE plus fulvestrant, and in 6 of 172 (3%) patients receiving placebo plus fulvestrant. Adverse reactions leading to discontinuation for those patients receiving IBRANCE plus fulvestrant included fatigue (0.6%), infections (0.6%), and thrombocytopenia (0.6%).

The most common adverse reactions (≥10%) of any grade reported in patients in the IBRANCE plus fulvestrant arm by descending frequency were neutropenia, leukopenia, infections, fatigue, nausea, anemia, stomatitis, diarrhea, thrombocytopenia, vomiting, alopecia, rash, decreased appetite, and pyrexia.

The most frequently reported Grade ≥3 adverse reactions (≥5%) in patients receiving IBRANCE plus fulvestrant in descending frequency were neutropenia and leukopenia.

Adverse reactions (≥10%) reported in patients who received IBRANCE plus fulvestrant or placebo plus fulvestrant in PALOMA-3 are listed in Table 6.

Table 6. Adverse Reactions (≥10%) in PALOMA-3
Adverse Reaction | IBRANCE plus Fulvestrant (N=345) |  |  | Placebo plus Fulvestrant (N=172)
Adverse Reaction | All Grades | Grade 3 | Grade 4 | All Grades | Grade 3 | Grade 4
Adverse Reaction | % | % | % | % | % | %
Infections and infestations
Infections [Infections includes all reported preferred terms (PTs) that are part of the System Organ Class Infections and infestations.] | 47 [Most common infections (≥1%) include: nasopharyngitis, upper respiratory infection, urinary tract infection, bronchitis, rhinitis, influenza, conjunctivitis, sinusitis, pneumonia, cystitis, oral herpes, respiratory tract infection, gastroenteritis, tooth infection, pharyngitis, eye infection, herpes simplex, and paronychia.] | 3 | 1 | 31 | 3 | 0
Blood and lymphatic system disorders
Neutropenia | 83 | 55 | 11 | 4 | 1 | 0
Leukopenia | 53 | 30 | 1 | 5 | 1 | 1
Anemia | 30 | 4 | 0 | 13 | 2 | 0
Thrombocytopenia | 23 | 2 | 1 | 0 | 0 | 0
Metabolism and nutrition disorders
Decreased appetite | 16 | 1 | 0 | 8 | 1 | 0
Gastrointestinal disorders
Nausea | 34 | 0 | 0 | 28 | 1 | 0
Stomatitis [Stomatitis includes: aphthous stomatitis, cheilitis, glossitis, glossodynia, mouth ulceration, mucosal inflammation, oral pain, oropharyngeal discomfort, oropharyngeal pain, stomatitis.] | 28 | 1 | 0 | 13 | 0 | 0
Diarrhea | 24 | 0 | 0 | 19 | 1 | 0
Vomiting | 19 | 1 | 0 | 15 | 1 | 0
Skin and subcutaneous tissue disorders
Alopecia | 18 [Grade 1 events – 17%; Grade 2 events – 1%.] | N/A | N/A | 6 [Grade 1 events – 6%.] | N/A | N/A
Rash [Rash includes: rash, rash maculo-papular, rash pruritic, rash erythematous, rash papular, dermatitis, dermatitis acneiform, toxic skin eruption.] | 17 | 1 | 0 | 6 | 0 | 0
General disorders and administration site conditions
Fatigue | 41 | 2 | 0 | 29 | 1 | 0
Pyrexia | 13 | <1 | 0 | 5 | 0 | 0
Grading according to CTCAE 4.0.
CTCAE=Common Terminology Criteria for Adverse Events; N=number of patients; N/A=not applicable.

Clinically relevant adverse reactions in <10% of patients who received IBRANCE plus fulvestrant in PALOMA-3 included asthenia (8%), dysgeusia (7%), epistaxis (7%), lacrimation increased (6%), dry skin (6%), vision blurred (6%), dry eye (3.8%), and febrile neutropenia (0.9%).

Table 7. Laboratory Abnormalities in PALOMA-3
Laboratory Abnormality | IBRANCE plus Fulvestrant (N=345) |  |  | Placebo plus Fulvestrant (N=172)
Laboratory Abnormality | All Grades % | Grade 3 % | Grade 4 % | All Grades % | Grade 3 % | Grade 4 %
WBC decreased | 99 | 45 | 1 | 26 | 0 | 1
Neutrophils decreased | 96 | 56 | 11 | 14 | 0 | 1
Blood creatinine increased | 95 | 1 | 0 | 82 | 0 | 0
Hemoglobin decreased | 78 | 3 | 0 | 40 | 2 | 0
Platelets decreased | 62 | 2 | 1 | 10 | 0 | 0
Aspartate aminotransferase increased | 43 | 4 | 0 | 48 | 4 | 0
Alanine aminotransferase increased | 36 | 2 | 0 | 34 | 0 | 0
N=number of patients; WBC=white blood cells.

INAVO120: IBRANCE plus Inavolisib and Fulvestrant

Adults with PIK3CA-mutated, HR-positive, HER2-negative, locally advanced or metastatic breast cancer whose disease progressed during or within 12 months of completing adjuvant endocrine therapy and who have not received prior systemic therapy for locally advanced or metastatic disease

The safety of the combination of IBRANCE plus inavolisib and fulvestrant was evaluated in a randomized, double-blind, placebo-controlled study (INAVO120) in 324 patients with PIK3CA-mutated, HR-positive, HER2-negative, locally advanced or metastatic breast cancer [see Clinical Studies (14)].

Patients received either IBRANCE 125 mg orally once daily for 21 consecutive days followed by 7 days off treatment to comprise a cycle of 28 days plus fulvestrant in combination with inavolisib (n=162) or placebo (n=162). The median duration of treatment for IBRANCE plus inavolisib and fulvestrant was 9 months (range: 0 to 39 months).

Serious adverse reactions occurred in 24% of patients who received IBRANCE plus inavolisib and fulvestrant. Serious adverse reactions occurring in ≥1% of patients receiving IBRANCE plus inavolisib and fulvestrant included anemia (1.9%), diarrhea (1.2%), and urinary tract infection (1.2%).

Fatal adverse reactions occurred in 3.7% of patients who received IBRANCE plus inavolisib and fulvestrant, including (0.6% each) acute coronary syndrome, cerebral hemorrhage, cerebrovascular accident, COVID-19 infection, and gastrointestinal hemorrhage.

Permanent discontinuation of IBRANCE associated with an adverse reaction occurred in 8 of 162 (4.9%) patients receiving IBRANCE plus inavolisib and fulvestrant and in 0 of 162 patients receiving IBRANCE plus placebo and fulvestrant. Adverse reactions leading to discontinuation of IBRANCE in patients receiving IBRANCE plus inavolisib and fulvestrant were neutropenia, infections, alanine aminotransferase increased, gastric ulcer, intestinal perforation, hyperglycemia, type 2 diabetes mellitus, bone pain, musculoskeletal pain, transitional cell carcinoma, and acute kidney injury (0.6% each).

Dose reduction of IBRANCE due to an adverse reaction occurred in 38% of patients receiving IBRANCE plus inavolisib and fulvestrant and in 30% of patients receiving IBRANCE plus placebo and fulvestrant. Adverse reactions leading to dose reductions of IBRANCE in ≥2% patients receiving IBRANCE plus inavolisib and fulvestrant were neutropenia (30%), leukopenia (6%), and thrombocytopenia (3.7%).

Dose interruption of IBRANCE due to an adverse reaction occurred in 71% of patients receiving IBRANCE plus inavolisib and fulvestrant and in 61% of patients receiving IBRANCE plus placebo and fulvestrant. Adverse reactions leading to dose interruption of IBRANCE in ≥2% patients receiving IBRANCE plus inavolisib and fulvestrant were neutropenia (56%), infections (29%), leukopenia (12%), stomatitis (4.9%), anemia (6%), thrombocytopenia (4.3%), diarrhea (3.7%), pyrexia (3.1%), alanine aminotransferase increased (2.5%), hyperglycemia (2.5%), and nausea (2.5%).

The most common (≥20%) adverse reactions, including laboratory abnormalities, were decreased neutrophils, decreased hemoglobin, increased fasting glucose, decreased platelets, decreased lymphocytes, stomatitis, diarrhea, decreased calcium, fatigue, decreased potassium, increased creatinine, increased alanine aminotransferase (ALT), nausea, decreased sodium, decreased magnesium, rash, decreased appetite, COVID-19 infection, and headache.

Adverse reactions and laboratory abnormalities in INAVO120 are summarized in Table 8 and Table 9, respectively.

Table 8. Adverse Reactions (≥10% with ≥5% [All Grades] or ≥2% [Grade 3-4] Higher Incidence in the IBRANCE plus inavolisib and fulvestrant Arm) in INAVO120
Adverse Reaction | IBRANCE plus Inavolisib and Fulvestrant (N=162) |  | IBRANCE plus Placebo and Fulvestrant (N=162)
Adverse Reaction | All Grades (%) | Grade 3-4 (%) | All Grades (%) | Grade 3-4 (%)
Gastrointestinal Disorders
Stomatitis [Includes aphthous ulcer, glossitis, glossodynia, lip ulceration, mouth ulceration, mucosal inflammation, and stomatitis.] | 51 | 6 [No Grade 4 adverse reactions were observed.] | 27 | 0
Diarrhea | 48 | 3.7 | 16 | 0
Nausea | 28 | 0.6 | 17 | 0
Vomiting | 15 | 0.6 | 4.9 | 1.2
General Disorders and Administration Site Conditions
Fatigue | 38 | 1.9 | 25 | 1.2
Skin and Subcutaneous Tissue Disorders
Rash [Includes other related terms.] | 26 | 0 | 19 | 0
Alopecia | 19 | 0 | 6 | 0
Dry skin [Includes dry skin, skin fissures, xerosis, and xeroderma.] | 13 | 0 | 4.3 | 0
Metabolism and Nutrition Disorders
Decreased appetite | 24 | 0 | 9 | 0
Infections and Infestations
COVID-19 infection | 23 | 1.9 | 10 | 0.6
Urinary tract infection | 15 | 1.2 | 9 | 0
Nervous System Disorders
Headache | 22 | 0 | 14 | 0
Investigations
Decreased weight | 17 | 3.7 | 0.6 | 0

Clinically relevant adverse reactions occurring in <10% of patients who received the triplet combination of IBRANCE plus inavolisib and fulvestrant included abdominal pain, dry eye, dysgeusia, and dyspepsia.

Table 9. Select Laboratory Abnormalities (≥10% with a ≥2% [All Grades or Grade 3-4] Higher Incidence in the IBRANCE plus Inavolisib and Fulvestrant Arm) in INAVO120
Laboratory Abnormality | IBRANCE plus Inavolisib and Fulvestrant [The denominator used to calculate the rate varied from 122 to 160 based on the number of patients with a baseline value and at least one post-treatment value.] |  | IBRANCE plus Placebo and Fulvestrant [The denominator used to calculate the rate varied from 131 to 161 based on the number of patients with a baseline value and at least one post-treatment value.]
Laboratory Abnormality | All Grades (%) | Grade 3-4 (%) | All Grades (%) | Grade 3-4 (%)
Hematology
Neutrophils (total, absolute) decreased | 95 | 82 | 97 | 79
Hemoglobin decreased | 88 | 8 [No Grade 4 laboratory abnormalities were observed.] | 85 | 2.5
Platelets decreased | 8 | 16 | 71 | 3.7
Lymphocytes (absolute) decreased | 72 | 9 | 68 | 14
Chemistry
Glucose (fasting) increased [Grading according to CTCAE version 4.03.] | 85 | 12 | 43 | 0
Calcium decreased | 42 | 3.1 | 32 | 3.7
Potassium decreased | 38 | 6 | 21 | 0.6
Creatinine increased | 38 | 1.9 | 30 | 1.2
ALT increased | 34 | 3.1 | 29 | 1.2
Sodium decreased | 28 | 2.5 | 19 | 2.5
Magnesium decreased | 27 | 0.6 | 21 | 0
Lipase (fasting) increased | 16 | 1.4 | 7 | 0
ALT=alanine aminotransferase.

Other Clinical Trials Experience

The following adverse reaction has been reported following administration of IBRANCE: venous thromboembolism.

6.2 Postmarketing Experience

The following adverse reactions have been identified during post-approval use of IBRANCE. Because these reactions are reported voluntarily from a population of uncertain size, it is not always possible to reliably estimate their frequency or establish a causal relationship to drug exposure.

Respiratory Disorders: Interstitial lung disease (ILD)/non-infectious pneumonitis

Skin and Subcutaneous Tissue Disorders: Palmar-plantar erythrodysesthesia syndrome (PPES)

Male Patients with HR-Positive, HER2-Negative Advanced or Metastatic Breast Cancer

Based on limited data from postmarketing reports and electronic health records, the safety profile for men treated with IBRANCE is consistent with the safety profile in women treated with IBRANCE.

7 DRUG INTERACTIONS

Palbociclib is primarily metabolized by CYP3A and sulfotransferase (SULT) enzyme SULT2A1. In vivo, palbociclib is a time-dependent inhibitor of CYP3A.

7.1 Agents That May Increase Palbociclib Plasma Concentrations

Effect of CYP3A Inhibitors

Coadministration of a strong CYP3A inhibitor (itraconazole) increased the plasma exposure of palbociclib in healthy subjects by 87%. Avoid concomitant use of strong CYP3A inhibitors (e.g., clarithromycin, indinavir, itraconazole, ketoconazole, lopinavir/ritonavir, nefazodone, nelfinavir, posaconazole, ritonavir, saquinavir, telaprevir, telithromycin, and voriconazole). Avoid grapefruit or grapefruit juice during IBRANCE treatment. If coadministration of IBRANCE with a strong CYP3A inhibitor cannot be avoided, reduce the dose of IBRANCE [see Dosage and Administration (2.2) and Clinical Pharmacology (12.3)].

7.2 Agents That May Decrease Palbociclib Plasma Concentrations

Effect of CYP3A Inducers

Coadministration of a strong CYP3A inducer (rifampin) decreased the plasma exposure of palbociclib in healthy subjects by 85%. Avoid concomitant use of strong CYP3A inducers (e.g., phenytoin, rifampin, carbamazepine, enzalutamide, and St John's Wort) [see Clinical Pharmacology (12.3)].

7.3 Drugs That May Have Their Plasma Concentrations Altered by Palbociclib

Coadministration of midazolam with multiple doses of IBRANCE increased the midazolam plasma exposure by 61%, in healthy subjects, compared to administration of midazolam alone. The dose of the sensitive CYP3A substrate with a narrow therapeutic index (e.g., alfentanil, cyclosporine, dihydroergotamine, ergotamine, everolimus, fentanyl, pimozide, quinidine, sirolimus, and tacrolimus) may need to be reduced, as IBRANCE may increase its exposure [see Clinical Pharmacology (12.3)].

8 USE IN SPECIFIC POPULATIONS

8.1 Pregnancy

Risk Summary

Based on findings from animal studies and its mechanism of action, IBRANCE can cause fetal harm when administered to a pregnant woman [see Clinical Pharmacology (12.1)]. There are no available data in pregnant women to inform the drug-associated risk. In animal reproduction studies, administration of palbociclib to pregnant rats and rabbits during organogenesis resulted in embryo-fetal toxicity at maternal exposures that were ≥4 times the human clinical exposure based on AUC (see Data). Advise pregnant women of the potential risk to a fetus.

The estimated background risk of major birth defects and miscarriage for the indicated population is unknown. In the U.S. general population, the estimated background risk of major birth defects and miscarriage in clinically recognized pregnancies is 2%–4% and 15%–20%, respectively.

Data

Animal Data

In a fertility and early embryonic development study in female rats, palbociclib was administered orally for 15 days before mating through to Day 7 of pregnancy, which did not cause embryo toxicity at doses up to 300 mg/kg/day with maternal systemic exposures approximately 4 times the human exposure (AUC) at the recommended dose.

In embryo-fetal development studies in rats and rabbits, pregnant animals received oral doses of palbociclib up to 300 mg/kg/day and 20 mg/kg/day, respectively, during the period of organogenesis. The maternally toxic dose of 300 mg/kg/day was fetotoxic in rats, resulting in reduced fetal body weights. At doses ≥100 mg/kg/day in rats, there was an increased incidence of a skeletal variation (increased incidence of a rib present at the seventh cervical vertebra). At the maternally toxic dose of 20 mg/kg/day in rabbits, there was an increased incidence of skeletal variations, including small phalanges in the forelimb. At 300 mg/kg/day in rats and 20 mg/kg/day in rabbits, the maternal systemic exposures were approximately 4 and 9 times the human exposure (AUC) at the recommended dose, respectively.

CDK4/6 double knockout mice have been reported to die in late stages of fetal development (gestation Day 14.5 until birth) due to severe anemia. However, knockout mouse data may not be predictive of effects in humans due to differences in degree of target inhibition.

8.2 Lactation

Risk Summary

There is no information regarding the presence of palbociclib in human milk, its effects on milk production, or the breastfed infant. Because of the potential for serious adverse reactions in breastfed infants from IBRANCE, advise a lactating woman not to breastfeed during treatment with IBRANCE and for 3 weeks after the last dose.

8.3 Females and Males of Reproductive Potential

Pregnancy Testing

Based on animal studies, IBRANCE can cause fetal harm when administered to a pregnant woman [see Use in Specific Populations (8.1)]. Females of reproductive potential should have a pregnancy test prior to starting treatment with IBRANCE.

Contraception

Females

IBRANCE can cause fetal harm when administered to a pregnant woman [see Use in Specific Populations (8.1)]. Advise females of reproductive potential to use effective contraception during treatment with IBRANCE and for at least 3 weeks after the last dose.

Males

Because of the potential for genotoxicity, advise male patients with female partners of reproductive potential to use effective contraception during treatment with IBRANCE and for 3 months after the last dose [see Nonclinical Toxicology (13.1)].

Infertility

Males

Based on animal studies, IBRANCE may impair fertility in males of reproductive potential [see Nonclinical Toxicology (13.1)].

8.4 Pediatric Use

The safety and effectiveness of IBRANCE in pediatric patients have not been established.

The safety and effectiveness of IBRANCE were assessed but not established in three trials: one open-label trial [A5481092, (NCT03709680)] that included 98 pediatric patients 2 to <17 years of age who received IBRANCE in combination with chemotherapy for recurrent or refractory solid tumors and two open-label trials that included 42 pediatric patients 4 to <17 years of age who received IBRANCE as a single agent for recurrent or refractory solid tumors [APEC1621I, (NCT03526250)] or primary central nervous system (CNS) tumors [PBTC-042, (NCT02255461)].

No new safety signals were observed in these trials. Palbociclib exposures in pediatric patients who received IBRANCE as a single agent or in combination were within range of those observed in adults given a similar dose based on body surface area.

Juvenile Animal Toxicity Data

Altered glucose metabolism (glycosuria, hyperglycemia, decreased insulin) associated with changes in the pancreas (islet cell vacuolation), eye (cataracts, lens degeneration), kidney (tubule vacuolation, chronic progressive nephropathy) and adipose tissue (atrophy) were identified in a 27 week repeat-dose toxicology study in rats that were immature at the beginning of the studies and were most prevalent in males at oral palbociclib doses ≥30 mg/kg/day (approximately 11 times the adult human exposure [AUC] at the recommended dose). Some of these findings (glycosuria/hyperglycemia, pancreatic islet cell vacuolation, and kidney tubule vacuolation) were present with lower incidence and severity in a 15 week repeat-dose toxicology study in immature rats. Altered glucose metabolism or associated changes in the pancreas, eye, kidney and adipose tissue were not identified in a 27-week repeat-dose toxicology study in rats that were mature at the beginning of the study and in dogs in repeat-dose toxicology studies up to 39 weeks duration.

Toxicities in teeth independent of altered glucose metabolism were observed in rats. Administration of 100 mg/kg palbociclib for 27 weeks (approximately 15 times the adult human exposure [AUC] at the recommended dose) resulted in abnormalities in growing incisor teeth (discolored, ameloblast degeneration/necrosis, mononuclear cell infiltrate). Other toxicities of potential concern to pediatric patients have not been evaluated in juvenile animals.

8.5 Geriatric Use

Of 444 patients who received IBRANCE in PALOMA-2, 181 patients (41%) were ≥65 years of age and 48 patients (11%) were ≥75 years of age. Of 347 patients who received IBRANCE in PALOMA-3, 86 patients (25%) were ≥65 years of age and 27 patients (8%) were ≥75 years of age. No overall differences in safety or effectiveness of IBRANCE were observed between these patients and younger patients.

8.6 Hepatic Impairment

No dose adjustment is required in patients with mild or moderate hepatic impairment (Child-Pugh classes A and B). For patients with severe hepatic impairment (Child-Pugh class C), the recommended dose of IBRANCE is 75 mg once daily for 21 consecutive days followed by 7 days off treatment to comprise a complete cycle of 28 days [see Dosage and Administration (2.2)]. Based on a pharmacokinetic trial in subjects with varying degrees of hepatic function, the palbociclib unbound exposure (unbound AUCINF) decreased by 17% in subjects with mild hepatic impairment (Child-Pugh class A), and increased by 34% and 77% in subjects with moderate (Child-Pugh class B) and severe (Child-Pugh class C) hepatic impairment, respectively, relative to subjects with normal hepatic function. Peak palbociclib unbound exposure (unbound Cmax) increased by 7%, 38% and 72% for mild, moderate and severe hepatic impairment, respectively, relative to subjects with normal hepatic function [see Clinical Pharmacology (12.3)].

Review the Full Prescribing Information for the aromatase inhibitor or fulvestrant for dose modifications related to hepatic impairment.

8.7 Renal Impairment

No dose adjustment is required in patients with mild, moderate, or severe renal impairment (CrCl >15 mL/min).

Based on a pharmacokinetic trial in subjects with varying degrees of renal function, the total palbociclib exposure (AUCINF) increased by 39%, 42%, and 31% with mild (60 mL/min ≤ CrCl <90 mL/min), moderate (30 mL/min ≤ CrCl <60 mL/min), and severe (CrCl <30 mL/min) renal impairment, respectively, relative to subjects with normal renal function. Peak palbociclib exposure (Cmax) increased by 17%, 12%, and 15% for mild, moderate, and severe renal impairment, respectively, relative to subjects with normal renal function.

The pharmacokinetics of palbociclib have not been studied in patients requiring hemodialysis [see Clinical Pharmacology (12.3)].

11 DESCRIPTION

IBRANCE tablets for oral administration contain 125 mg, 100 mg, or 75 mg of palbociclib, a kinase inhibitor. The molecular formula for palbociclib is C24H29N7O2. The molecular weight is 447.54 daltons. The chemical name is 6-acetyl-8-cyclopentyl-5-methyl-2-{[5-(piperazin-1-yl)pyridin-2-yl]amino}pyrido[2,3-d]pyrimidin-7(8H)-one, and its structural formula is:

Palbociclib is a yellow to orange powder. At or below pH 4, palbociclib behaves as a high-solubility compound. Above pH 4, the solubility of the drug substance reduces significantly.

Inactive Ingredients: Microcrystalline cellulose, colloidal silicon dioxide, crospovidone, magnesium stearate, succinic acid, HPMC 2910/hypromellose, titanium dioxide, triacetin, and FD&C Blue #2/Indigo Carmine Aluminum Lake. In addition, the 75 mg and 125 mg tablets contain red iron oxide and the 100 mg tablets contain yellow iron oxide.

12 CLINICAL PHARMACOLOGY

12.1 Mechanism of Action

Palbociclib is an inhibitor of cyclin-dependent kinases (CDK) 4 and 6. Cyclin D1 and CDK4/6 are downstream of signaling pathways which lead to cellular proliferation. In vitro, palbociclib reduced cellular proliferation of estrogen receptor (ER)-positive breast cancer cell lines by blocking progression of the cell from G1 into S phase of the cell cycle. Treatment of breast cancer cell lines with the combination of palbociclib and antiestrogens leads to decreased retinoblastoma (Rb) protein phosphorylation resulting in reduced E2F expression and signaling, and increased growth arrest compared to treatment with each drug alone. In vitro treatment of ER-positive breast cancer cell lines with the combination of palbociclib and antiestrogens led to increased cell senescence compared to each drug alone, which was sustained for up to 6 days following palbociclib removal and was greater if antiestrogen treatment was continued. In vivo studies using a patient-derived ER-positive breast cancer xenograft model demonstrated that the combination of palbociclib and letrozole increased the inhibition of Rb phosphorylation, downstream signaling, and tumor growth compared to each drug alone.

Human bone marrow mononuclear cells treated with palbociclib in the presence or absence of an anti-estrogen in vitro did not become senescent and resumed proliferation following palbociclib withdrawal.

12.2 Pharmacodynamics

Cardiac Electrophysiology

The effect of palbociclib on the QT interval corrected for heart rate (QTc) was evaluated using time-matched electrocardiograms (ECGs) evaluating the change from baseline and corresponding pharmacokinetic data in 77 patients with breast cancer. Palbociclib had no large effect on QTc (i.e., >20 ms) at 125 mg once daily for 21 consecutive days followed by 7 days off treatment to comprise a complete cycle of 28 days.

12.3 Pharmacokinetics

The pharmacokinetics (PK) of palbociclib were characterized in patients with solid tumors including advanced breast cancer and in healthy subjects.

Absorption

The maximum observed concentration (Cmax) of palbociclib is generally observed between 4 to 12 hours (time to reach maximum concentration, Tmax) following oral administration of IBRANCE tablets. The mean absolute bioavailability of IBRANCE after an oral 125 mg dose is 46%. In the dosing range of 25 mg to 225 mg, the AUC and Cmax increased proportionally with dose in general. Steady state was achieved within 8 days following repeated once daily dosing. With repeated once daily administration, palbociclib accumulated with a median accumulation ratio of 2.4 (range 1.5 to 4.2).

Food Effect: The area under the concentration-time curve from zero to infinity (AUCINF) and Cmax of palbociclib increased by 22% and 26%, respectively, when IBRANCE tablets were given with a high-fat, high-calorie meal (approximately 800 to 1000 calories with 150, 250, and 500 to 600 calories from protein, carbohydrate, and fat, respectively), and by 9% and 10%, respectively, when IBRANCE tablets were given with a moderate-fat, standard-calorie meal (approximately 500 to 700 calories with 75 to 105, 250 to 350 and 175 to 245 calories from protein, carbohydrate, and fat, respectively), compared to IBRANCE tablets given under overnight fasted conditions.

Distribution

Binding of palbociclib to human plasma proteins in vitro was approximately 85%, with no concentration dependence over the concentration range of 500 ng/mL to 5000 ng/mL. The mean fraction unbound (fu) of palbociclib in human plasma in vivo increased incrementally with worsening hepatic function. There was no obvious trend in the mean palbociclib fu in human plasma in vivo with worsening renal function. The geometric mean apparent volume of distribution (Vz/F) was 2583 L with a coefficient of variation (CV) of 26%.

Metabolism

In vitro and in vivo studies indicated that palbociclib undergoes hepatic metabolism in humans. Following oral administration of a single 125 mg dose of [^14C]palbociclib to humans, the primary metabolic pathways for palbociclib involved oxidation and sulfonation, with acylation and glucuronidation contributing as minor pathways. Palbociclib was the major circulating drug-derived entity in plasma (23%). The major circulating metabolite was a glucuronide conjugate of palbociclib, although it only represented 1.5% of the administered dose in the excreta. Palbociclib was extensively metabolized with unchanged drug accounting for 2.3% and 6.9% of radioactivity in feces and urine, respectively. In feces, the sulfamic acid conjugate of palbociclib was the major drug-related component, accounting for 26% of the administered dose. In vitro studies with human hepatocytes, liver cytosolic and S9 fractions, and recombinant SULT enzymes indicated that CYP3A and SULT2A1 are mainly involved in the metabolism of palbociclib.

Elimination

The geometric mean apparent oral clearance (CL/F) of palbociclib was 63.1 L/hr (29% CV), and the mean (± standard deviation) plasma elimination half-life was 29 (±5) hours in patients with advanced breast cancer. In 6 healthy male subjects given a single oral dose of [^14C] palbociclib, a median of 91.6% of the total administered radioactive dose was recovered in 15 days; feces (74.1% of dose) was the major route of excretion, with 17.5% of the dose recovered in urine. The majority of the material was excreted as metabolites.

Specific Populations

Age, Gender, and Body Weight

Based on a population pharmacokinetic analysis in 183 patients with cancer (50 male and 133 female patients, age range from 22 to 89 years, and body weight range from 37.9 to 123 kg), gender had no effect on the exposure of palbociclib, and age and body weight had no clinically important effect on the exposure of palbociclib.

Hepatic Impairment

Data from a pharmacokinetic trial in subjects with varying degrees of hepatic impairment indicate that palbociclib unbound AUCINF decreased 17% in subjects with mild hepatic impairment (Child-Pugh class A), and increased by 34% and 77% in subjects with moderate (Child-Pugh class B) and severe (Child-Pugh class C) hepatic impairment, respectively, relative to subjects with normal hepatic function. Palbociclib unbound Cmax increased by 7%, 38% and 72% for mild, moderate and severe hepatic impairment, respectively, relative to subjects with normal hepatic function. In addition, based on a population pharmacokinetic analysis that included 183 patients, where 40 patients had mild hepatic impairment based on National Cancer Institute (NCI) classification (total bilirubin ≤ ULN and AST > ULN, or total bilirubin >1.0 to 1.5 × ULN and any AST), mild hepatic impairment had no effect on the exposure of palbociclib, further supporting the findings from the dedicated hepatic impairment study.

Renal Impairment

Data from a pharmacokinetic trial in subjects with varying degrees of renal impairment indicate that palbociclib AUCINF increased by 39%, 42%, and 31% with mild (60 mL/min ≤ CrCl <90 mL/min), moderate (30 mL/min ≤ CrCl <60 mL/min), and severe (CrCl <30 mL/min) renal impairment, respectively, relative to subjects with normal renal function. Peak palbociclib exposure (Cmax) increased by 17%, 12%, and 15% for mild, moderate, and severe renal impairment, respectively, relative to subjects with normal renal function. In addition, based on a population pharmacokinetic analysis that included 183 patients where 73 patients had mild renal impairment and 29 patients had moderate renal impairment, mild and moderate renal impairment had no effect on the exposure of palbociclib. The pharmacokinetics of palbociclib have not been studied in patients requiring hemodialysis.

Drug Interactions

In vitro data indicate that CYP3A and SULT enzyme SULT2A1 are mainly involved in the metabolism of palbociclib. Palbociclib is a weak time-dependent inhibitor of CYP3A following daily 125 mg dosing to steady state in humans. In vitro, palbociclib is not an inhibitor of CYP1A2, 2A6, 2B6, 2C8, 2C9, 2C19, and 2D6, and is not an inducer of CYP1A2, 2B6, 2C8, and 3A4 at clinically relevant concentrations.

CYP3A Inhibitors: Data from a drug interaction trial in healthy subjects (N=12) indicate that coadministration of multiple 200 mg daily doses of itraconazole with a single 125 mg IBRANCE dose increased palbociclib AUCINF and the Cmax by approximately 87% and 34%, respectively, relative to a single 125 mg IBRANCE dose given alone [see Drug Interactions (7.1)].

CYP3A Inducers: Data from a drug interaction trial in healthy subjects (N=15) indicate that coadministration of multiple 600 mg daily doses of rifampin, a strong CYP3A inducer, with a single 125 mg IBRANCE dose decreased palbociclib AUCINF and Cmax by 85% and 70%, respectively, relative to a single 125 mg IBRANCE dose given alone. Data from a drug interaction trial in healthy subjects (N=14) indicate that coadministration of multiple 400 mg daily doses of modafinil, a moderate CYP3A inducer, with a single 125 mg IBRANCE dose decreased palbociclib AUCINF and Cmax by 32% and 11%, respectively, relative to a single 125 mg IBRANCE dose given alone [see Drug Interactions (7.2)].

CYP3A Substrates: Palbociclib is a weak time-dependent inhibitor of CYP3A following daily 125 mg dosing to steady state in humans. In a drug interaction trial in healthy subjects (N=26), coadministration of midazolam with multiple doses of IBRANCE increased the midazolam AUCINF and the Cmax values by 61% and 37%, respectively, as compared to administration of midazolam alone [see Drug Interactions (7.3)].

Gastric pH Elevating Medications: In a drug interaction trial in healthy subjects, coadministration of a single 125 mg IBRANCE tablet with multiple doses of the proton pump inhibitor (PPI) rabeprazole under overnight fasted conditions had no effect on the rate and extent of absorption of palbociclib when compared to a single 125 mg IBRANCE tablet administered alone. Given the reduced effect on gastric pH of H2-receptor antagonists and local antacids compared to PPIs, an effect of these classes of acid reducing agents on palbociclib exposure is not expected.

Effect of Palbociclib on Transporters: In vitro evaluations indicated that palbociclib has a low potential to inhibit the activities of drug transporters organic anion transporter (OAT)1, OAT3, organic cation transporter (OCT)2, and organic anion transporting polypeptide (OATP)1B1, OATP1B3 at clinically relevant concentrations. In vitro, palbociclib has the potential to inhibit OCT1 at clinically relevant concentrations, as well as the potential to inhibit P-glycoprotein (P-gp) or breast cancer resistance protein (BCRP) in the gastrointestinal tract at the proposed dose.

Effect of Transporters on Palbociclib: Based on in vitro data, P-gp and BCRP mediated transport are unlikely to affect the extent of oral absorption of palbociclib at therapeutic doses.

13 NONCLINICAL TOXICOLOGY

13.1 Carcinogenesis, Mutagenesis, Impairment of Fertility

Palbociclib was assessed for carcinogenicity in a 6-month transgenic mouse study and in a 2-year rat study. Oral administration of palbociclib for 2 years resulted in an increased incidence of microglial cell tumors in the central nervous system of male rats at a dose of 30 mg/kg/day (approximately 8 times the human clinical exposure based on AUC). There were no neoplastic findings in female rats at doses up to 200 mg/kg/day (approximately 5 times the human clinical exposure based on AUC). Oral administration of palbociclib to male and female rasH2 transgenic mice for 6 months did not result in increased incidence of neoplasms at doses up to 60 mg/kg/day.

Palbociclib was aneugenic in Chinese Hamster Ovary cells in vitro and in the bone marrow of male rats at doses ≥100 mg/kg/day for 3 weeks. Palbociclib was not mutagenic in an in vitro bacterial reverse mutation (Ames) assay and was not clastogenic in the in vitro human lymphocyte chromosome aberration assay.

In a fertility study in female rats, palbociclib did not affect mating or fertility at any dose up to 300 mg/kg/day (approximately 4 times human clinical exposure based on AUC) and no adverse effects were observed in the female reproductive tissues in repeat-dose toxicity studies up to 300 mg/kg/day in the rat and 3 mg/kg/day in the dog (approximately 6 times and similar to human exposure [AUC], at the recommended dose, respectively).

The adverse effects of palbociclib on male reproductive function and fertility were observed in the repeat-dose toxicology studies in rats and dogs and a male fertility study in rats. In repeat-dose toxicology studies, palbociclib-related findings in the testis, epididymis, prostate, and seminal vesicle at ≥30 mg/kg/day in rats and ≥0.2 mg/kg/day in dogs included decreased organ weight, atrophy or degeneration, hypospermia, intratubular cellular debris, and decreased secretion. Partial reversibility of male reproductive organ effects was observed in the rat and dog following a 4- and 12-week non-dosing period, respectively. These doses in rats and dogs resulted in approximately ≥10 and 0.1 times, respectively, the exposure [AUC] in humans at the recommended dose. In the fertility and early embryonic development study in male rats, palbociclib caused no effects on mating but resulted in a slight decrease in fertility in association with lower sperm motility and density at 100 mg/kg/day with projected exposure levels [AUC] of 20 times the exposure in humans at the recommended dose.

14 CLINICAL STUDIES

PALOMA-2: IBRANCE plus Letrozole

Patients with ER-positive, HER2-negative advanced or metastatic breast cancer for initial endocrine-based therapy

PALOMA-2 was an international, randomized, double-blind, parallel-group, multicenter study of IBRANCE plus letrozole versus placebo plus letrozole conducted in postmenopausal women with ER-positive, HER2-negative advanced breast cancer who had not received previous systemic treatment for their advanced disease. A total of 666 patients were randomized 2:1 to IBRANCE plus letrozole or placebo plus letrozole. Randomization was stratified by disease site (visceral versus non-visceral), disease-free interval (de novo metastatic versus ≤12 months from the end of adjuvant treatment to disease recurrence versus >12 months from the end of adjuvant treatment to disease recurrence), and nature of prior (neo)adjuvant anticancer therapies (prior hormonal therapies versus no prior hormonal therapy). IBRANCE was given orally at a dose of 125 mg daily for 21 consecutive days followed by 7 days off treatment. Patients received study treatment until objective disease progression, symptomatic deterioration, unacceptable toxicity, death, or withdrawal of consent, whichever occurred first. The major efficacy outcome of the study was investigator-assessed progression-free survival (PFS) evaluated according to Response Evaluation Criteria in Solid Tumors Version 1.1 (RECIST). Additional efficacy outcome measures were confirmed overall response rate (ORR) as assessed by the investigator according to RECIST Version 1.1 and overall survival (OS).

Patients enrolled in this study had a median age of 62 years (range 28 to 89). The majority of patients were White (78%), and most patients had an Eastern Cooperative Oncology Group (ECOG) performance status (PS) of 0 or 1 (98%). Forty-eight percent of patients had received chemotherapy and 56% had received antihormonal therapy in the neoadjuvant or adjuvant setting prior to their diagnosis of advanced breast cancer. Thirty-seven percent of patients had no prior systemic therapy in the neoadjuvant or adjuvant setting. The majority of patients (97%) had metastatic disease. Twenty-three percent of patients had bone only disease, and 49% of patients had visceral disease.

Major efficacy results from PALOMA-2 are summarized in Table 10 and Figure 1. Consistent results were observed across patient subgroups of disease-free interval (DFI), disease site, and prior therapy. The treatment effect of the combination on PFS was also supported by an independent review of radiographs. Based on the prespecified final OS analysis conducted after 435 events, OS was not statistically significant.

Table 10. Efficacy Results – PALOMA-2
 | IBRANCE plus Letrozole | Placebo plus Letrozole
Progression-free survival for ITT (investigator assessment) | N=444 | N=222
Number of PFS events (%) | 194 (43.7) | 137 (61.7)
Median progression-free survival (months, 95% CI) | 24.8 (22.1, NE) | 14.5 (12.9, 17.1)
Hazard ratio (95% CI) and p-value | 0.576 (0.463, 0.718) [Cox proportional hazards model stratified by disease site (visceral vs. non-visceral) per randomization.] , p<0.0001 [Stratified log-rank test one-sided p-value.]
Objective Response for patients with measurable disease (investigator assessment) | N=338 | N=171
Objective response rate [Response is based on confirmed responses.] (%, 95% CI) | 55.3 (49.9, 60.7) | 44.4 (36.9, 52.2)
Overall survival for ITT | N=444 | N=222
Number of OS events (%) | 287 (64.6) | 148 (66.7)
Median OS (months, 95% CI) | 53.8 (49.8, 59.2) | 49.8 (42.3, 56.4)
Hazard ratio (95% CI) and p‑value | 0.921 (0.755, 1.124), p=0.2087
CI=confidence interval; ITT=Intent-to-Treat; N=number of patients; NE=not estimable; OS=Overall survival; PFS=Progression‑free survival.

Figure 1. Kaplan-Meier Plot of Progression-Free Survival – PALOMA-2 (Investigator Assessment, Intent-to-Treat Population)

LET=letrozole; PAL=palbociclib; PBO=placebo.

PALOMA-3: IBRANCE plus Fulvestrant

Patients with HR-positive, HER2-negative advanced or metastatic breast cancer who have had disease progression on or after prior adjuvant or metastatic endocrine therapy

PALOMA-3 was an international, randomized, double-blind, parallel-group, multicenter study of IBRANCE plus fulvestrant versus placebo plus fulvestrant conducted in women with HR-positive, HER2-negative advanced breast cancer, regardless of their menopausal status, whose disease progressed on or after prior endocrine therapy. A total of 521 pre/postmenopausal women were randomized 2:1 to IBRANCE plus fulvestrant or placebo plus fulvestrant and stratified by documented sensitivity to prior hormonal therapy, menopausal status at study entry (pre/peri versus postmenopausal), and presence of visceral metastases. IBRANCE was given orally at a dose of 125 mg daily for 21 consecutive days followed by 7 days off treatment. Pre/perimenopausal women were enrolled in the study and received the LHRH agonist goserelin for at least 4 weeks prior to and for the duration of PALOMA-3. Patients continued to receive assigned treatment until objective disease progression, symptomatic deterioration, unacceptable toxicity, death, or withdrawal of consent, whichever occurred first. The major efficacy outcome of the study was investigator-assessed PFS evaluated according to RECIST 1.1.

Patients enrolled in this study had a median age of 57 years (range 29 to 88). The majority of patients on study were White (74%), all patients had an ECOG PS of 0 or 1, and 80% were postmenopausal. All patients had received prior systemic therapy, and 75% of patients had received a previous chemotherapy regimen. Twenty-five percent of patients had received no prior therapy in the metastatic disease setting, 60% had visceral metastases, and 23% had bone only disease.

The results from the investigator-assessed PFS and final OS from PALOMA-3 are summarized in Table 11. The relevant Kaplan-Meier plots are shown in Figures 2 and 3, respectively. Consistent PFS results were observed across patient subgroups of disease site, sensitivity to prior hormonal therapy, and menopausal status. After a median follow-up time of 45 months, the final OS results were not statistically significant.

Table 11. Efficacy Results – PALOMA-3
 | IBRANCE plus Fulvestrant | Placebo plus Fulvestrant
Progression-free survival for ITT (investigator assessment) | N=347 | N=174
Number of PFS events (%) | 145 (41.8) | 114 (65.5)
Median PFS (months, 95% CI) | 9.5 (9.2, 11.0) | 4.6 (3.5, 5.6)
Hazard ratio (95% CI) and p-value | 0.461 (0.360, 0.591), p<0.0001
Objective Response for patients with measurable disease (investigator assessment) | N=267 | N=138
Objective response rate [Responses are based on confirmed responses.] (%, 95% CI) | 24.6 (19.6, 30.2) | 10.9 (6.2, 17.3)
Overall survival for ITT | N=347 | N=174
Number of OS events (%) | 201 (57.9) | 109 (62.6)
Median OS (months, 95% CI) | 34.9 (28.8, 40.0) | 28.0 (23.6, 34.6)
Hazard ratio (95% CI) and p-value | 0.814 (0.644, 1.029), p=0.0857 [Not statistically significant at the pre-specified 2-sided alpha level of 0.047.] [2-sided p-value from the log-rank test stratified by the presence of visceral metastases and sensitivity to prior endocrine therapy per randomization.]
CI=confidence interval; ITT=Intent-to-Treat; N=number of patients; OS=overall survival; PFS=progression-free survival.

Figure 2. Kaplan-Meier Plot of Progression-Free Survival – PALOMA-3 (Investigator Assessment, Intent-to-Treat Population)

FUL=fulvestrant; PAL=palbociclib; PBO=placebo.

Figure 3. Kaplan-Meier Plot of Overall Survival (Intent-to-Treat Population) – PALOMA-3

FUL=fulvestrant; PAL=palbociclib; PBO=placebo.

INAVO120: IBRANCE plus Inavolisib and Fulvestrant

Adults with PIK3CA-mutated, HR-positive, HER2-negative, locally advanced or metastatic breast cancer whose disease progressed during or within 12 months of completing adjuvant endocrine therapy and who have not received prior systemic therapy for locally advanced or metastatic disease

INAVO120 (NCT04191499) was a randomized (1:1), double-blind, placebo-controlled trial evaluating the efficacy of inavolisib in combination with IBRANCE and fulvestrant in adult patients with endocrine-resistant PIK3CA-mutated, HR-positive, HER2-negative (defined as IHC 0 or 1+, or IHC 2+/ISH-), locally advanced or metastatic breast cancer whose disease progressed during or within 12 months of completing adjuvant endocrine therapy and who have not received prior systemic therapy for locally advanced or metastatic disease. Randomization was stratified by presence of visceral disease (yes or no), endocrine resistance (primary or secondary), and geographic region (North America/Western Europe, Asia, other).

Primary endocrine resistance was defined as relapse while on the first 2 years of adjuvant endocrine therapy (ET) and secondary endocrine resistance was defined as relapse while on adjuvant ET after at least 2 years or relapse within 12 months of completing adjuvant ET.

Patients were required to have a HbA1C <6% and fasting blood glucose <126 mg/dL. The study excluded patients with Type 1 diabetes mellitus or Type 2 diabetes mellitus requiring ongoing anti-hyperglycemic treatment at the start of study treatment.

PIK3CA mutation status was prospectively determined in a central laboratory using the FoundationOne® Liquid CDx assay on plasma-derived circulating tumor DNA (ctDNA) or in local laboratories using various validated polymerase chain reaction (PCR) or next-generation sequencing (NGS) assays on tumor tissue or plasma. All patients were required to provide both a freshly collected pre-treatment blood sample and a tumor tissue sample for central evaluation and determination of PIK3CA mutation(s) status.

Patients received either inavolisib 9 mg (n=161) or placebo (n=164) orally once daily, in combination with IBRANCE 125 mg orally once daily for 21 consecutive days followed by 7 days off treatment to comprise a cycle of 28 days, and fulvestrant 500 mg administered intramuscularly on Cycle 1, Days 1 and 15, and then on Day 1 of every 28-day cycle. Patients received treatment until disease progression or unacceptable toxicity. In addition, all pre/perimenopausal women and men received an LHRH agonist throughout therapy.

The baseline demographic and disease characteristics were: median age 54 years (range: 27 to 79 years); 98% female, of which 39% were pre/perimenopausal; 59% White, 38% Asian, 2.5% Unknown, 0.6% Black or African American; 6% Hispanic or Latino; and ECOG PS of 0 (63%) or 1 (36%). Tamoxifen (57%) and aromatase inhibitors (50%) were the most commonly used adjuvant endocrine therapies. Sixty-four percent of patients were considered to have secondary endocrine resistance. Eighty-three percent of patients had received prior chemotherapy (in the neo/adjuvant setting) and 1.2% of patients had been treated with a CDK4/6 inhibitor.

The major efficacy outcome measure was investigator (INV)-assessed PFS per RECIST version 1.1. Additional efficacy outcome measures included OS, INV-assessed ORR, and INV-assessed duration of response (DOR).

Efficacy results are summarized in Table 12 and Figure 4. INV-assessed PFS results were supported by consistent results from a blinded independent central review (BICR) assessment. At the time of the PFS analysis, OS data were not mature with 30% deaths in the overall population.

Table 12. Efficacy Results in Patients with Locally Advanced or Metastatic Breast Cancer in INAVO120
Efficacy Endpoint | IBRANCE plus Inavolisib and Fulvestrant; N=161 | IBRANCE plus Placebo and Fulvestrant; N=164
Progression-Free Survival [Per RECIST version 1.1.] [Based on investigator assessment.]
Patients with event (%) | 82 (51) | 113 (69)
Median, months (95% CI) | 15.0 (11.3, 20.5) | 7.3 (5.6, 9.3)
Hazard ratio (95% CI) | 0.43 (0.32, 0.59)
p-value | <0.0001
Objective Response Rate [Based on confirmed ORR.]
Patients with CR or PR (%) | 94 (58) | 41 (25)
95% CI | (50, 66) | (19, 32)
Duration of Response
Median DOR, months (95% CI) | 18.4 (10.4, 22.2) | 9.6 (7.4, 16.6)
CI=confidence interval; CR=complete response; DOR=duration of response; N=number of patients; PR=partial response.

Figure 4. Kaplan-Meier Curve for Investigator-Assessed Progression-Free Survival in INAVO120

16 HOW SUPPLIED/STORAGE AND HANDLING

IBRANCE is supplied in the following strengths and package configurations:

IBRANCE Tablets
Package Configuration | Tablet Strength (mg) | NDC | Tablet Description
Monthly box containing 3 weekly blister packs of 7 tablets each (21 tablets total) | 125 | NDC 0069-0688-03 | Oval, light purple, film-coated tablets debossed with "Pfizer" on one side and "PBC 125" on the other side.
Monthly box containing 3 weekly blister packs of 7 tablets each (21 tablets total) | 100 | NDC 0069-0486-03 | Oval, green, film-coated tablets debossed with "Pfizer" on one side and "PBC 100" on the other side.
Monthly box containing 3 weekly blister packs of 7 tablets each (21 tablets total) | 75 | NDC 0069-0284-03 | Round, light purple, film-coated tablets debossed with "Pfizer" on one side and "PBC 75" on the other side.

STORAGE AND HANDLING

Store at 20°C to 25°C (68°F to 77°F); excursions permitted between 15°C to 30°C (59°F to 86°F) [see USP Controlled Room Temperature]. Store in the original blister pack.

17 PATIENT COUNSELING INFORMATION

Advise the patient to read the FDA-approved patient labeling (Patient Information).

Myelosuppression/Infection

- Advise patients to immediately report any signs or symptoms of myelosuppression or infection, such as fever, chills, dizziness, shortness of breath, weakness, or any increased tendency to bleed and/or to bruise [see Warnings and Precautions (5.1)].

Interstitial Lung Disease/Pneumonitis

- Advise patients to immediately report new or worsening respiratory symptoms [see Warnings and Precautions (5.2)].

Drug Interactions

- Grapefruit may interact with IBRANCE. Patients should not consume grapefruit products while on treatment with IBRANCE.
- Inform patients to avoid strong CYP3A inhibitors and strong CYP3A inducers.
- Advise patients to inform their healthcare providers of all concomitant medications, including prescription medicines, over-the-counter drugs, vitamins, and herbal products [see Drug Interactions (7)].

Dosing and Administration

- Inform patients that IBRANCE tablets may be taken with or without food.
- If the patient vomits or misses a dose, an additional dose should not be taken. The next prescribed dose should be taken at the usual time. IBRANCE tablets should be swallowed whole (do not chew, crush, or split them prior to swallowing). No tablet should be ingested if it is broken, cracked, or otherwise not intact.
- Pre/perimenopausal women treated with IBRANCE should also be treated with LHRH agonists [see Dosage and Administration (2.1)].
- When IBRANCE is used in combination, refer to the other products’ Full Prescribing Information for dosing and administration information [see Dosage and Administration (2.1, 2.2)].

Pregnancy, Lactation, and Infertility

- Embryo-Fetal Toxicity
  - Advise females of reproductive potential of the potential risk to a fetus and to use effective contraception during treatment with IBRANCE therapy and for at least 3 weeks after the last dose. Advise females to inform their healthcare provider of a known or suspected pregnancy [see Warnings and Precautions (5.3) and Use in Specific Populations (8.1 and 8.3)].
  - Advise male patients with female partners of reproductive potential to use effective contraception during treatment with IBRANCE and for at least 3 months after the last dose [see Use in Specific Populations (8.3)].
- Lactation: Advise women not to breastfeed during treatment with IBRANCE and for 3 weeks after the last dose [see Use in Specific Populations (8.2)].
- Infertility: Inform males of reproductive potential that IBRANCE may cause infertility and to consider sperm preservation before taking IBRANCE [see Use in Specific Populations (8.3)].

This product's labeling may have been updated. For full prescribing information, please visit www.pfizer.com. For medical information about IBRANCE, please visit www.pfizermedinfo.com or call 1-800-438-1985.

LAB-1371-7.0

PATIENT INFORMATION
IBRANCE® (EYE-brans)
(palbociclib)
Tablets

What is the most important information I should know about IBRANCE?

IBRANCE may cause serious side effects, including:

Low white blood cell counts (neutropenia). Low white blood cell counts are very common when taking IBRANCE and may cause serious infections that can lead to death. Your healthcare provider should check your white blood cell counts before and during treatment.

If you develop low white blood cell counts during treatment with IBRANCE, your healthcare provider may stop your treatment, decrease your dose, or may tell you to wait to begin your treatment cycle. Tell your healthcare provider right away if you have signs and symptoms of low white blood cell counts or infections such as fever and chills.

Lung problems (pneumonitis). IBRANCE may cause severe or life-threatening inflammation of the lungs during treatment that can lead to death. Tell your healthcare provider right away if you have any new or worsening symptoms, including:

- chest pain
- cough with or without mucus
- trouble breathing or shortness of breath

Your healthcare provider may interrupt or stop treatment with IBRANCE completely if your symptoms are severe.

See "What are the possible side effects of IBRANCE?" for more information about side effects.

What is IBRANCE?

IBRANCE is a prescription medicine used:

In adults to treat hormone receptor (HR)-positive, human epidermal growth factor receptor 2 (HER2)-negative breast cancer that has spread to other parts of the body (metastatic) in combination with:

- an aromatase inhibitor as the first hormonal based therapy, or
- fulvestrant in people with disease progression following hormonal therapy.

In adults with hormone receptor (HR)-positive, human epidermal growth factor receptor 2 (HER2)-negative and with an abnormal phosphatidylinositol-3-kinase catalytic subunit alpha (PIK3CA) gene breast cancer that has spread to nearby tissue or lymph nodes (locally advanced), or to other parts of the body (metastatic) in combination with:

- inavolisib and fulvestrant in people with disease progression during or after adjuvant hormonal therapy.

It is not known if IBRANCE is safe and effective in children.

What should I tell my healthcare provider before taking IBRANCE?

Before taking IBRANCE, tell your healthcare provider about all of your medical conditions, including if you:

- have fever, chills, or any other signs or symptoms of infection.
- have liver or kidney problems.
- have any other medical conditions.
- are pregnant, or plan to become pregnant. IBRANCE can harm your unborn baby.
  - Females who are able to become pregnant should use effective birth control during treatment and for at least 3 weeks after the last dose of IBRANCE. Your healthcare provider may ask you to take a pregnancy test before you start treatment with IBRANCE.
  - Males with female partners who can become pregnant should use effective birth control during treatment with IBRANCE for at least 3 months after the last dose of IBRANCE.
  - Talk to your healthcare provider about birth control methods that may be right for you during this time.
  - If you become pregnant or think you are pregnant, tell your healthcare provider right away.
- are breastfeeding or plan to breastfeed. It is not known if IBRANCE passes into your breast milk. Do not breastfeed during treatment with IBRANCE and for 3 weeks after the last dose.

Tell your healthcare provider about all of the medicines you take, including prescription and over-the-counter medicines, vitamins, and herbal supplements. IBRANCE and other medicines may affect each other causing side effects.

Know the medicines you take. Keep a list of them to show your healthcare provider or pharmacist when you get a new medicine.

How should I take IBRANCE?

- Take IBRANCE exactly as your healthcare provider tells you.
- IBRANCE tablets may be taken with or without food.
- IBRANCE should be taken at about the same time each day.
- Swallow IBRANCE tablets whole. Do not chew, crush or split IBRANCE tablets before swallowing them.
- Do not take any IBRANCE tablets that are broken, cracked, or that look damaged.
- Avoid grapefruit and grapefruit products during treatment with IBRANCE. Grapefruit may increase the amount of IBRANCE in your blood.
- Do not change your dose or stop taking IBRANCE unless your healthcare provider tells you.
- If you miss a dose of IBRANCE or vomit after taking a dose of IBRANCE, do not take another dose on that day. Take your next dose at your regular time.
- When IBRANCE is used in combination with inavolisib and fulvestrant, or an aromatase inhibitor, also read the Patient Information for the prescribed products.

What are the possible side effects of IBRANCE?

IBRANCE may cause serious side effects. See "What is the most important information I should know about IBRANCE?"

The most common side effects of IBRANCE when used with either letrozole or fulvestrant include:

- Low red blood cell counts and low platelet counts are common with IBRANCE. Call your healthcare provider right away if you develop any of these symptoms during treatment:

- dizziness
- shortness of breath
- weakness

- bleeding or bruising more easily
- nosebleeds

- infections (see "What is the most important information I should know about IBRANCE?")
- tiredness
- nausea
- sore mouth
- abnormalities in liver blood tests

- diarrhea
- hair thinning or hair loss
- increased blood creatinine

The most common side effects when inavolisib is added to IBRANCE plus fulvestrant include:

- high blood sugar levels leading to excessive thirst and urination
- sore mouth
- diarrhea
- decreased white blood cell counts, red blood cell counts, and platelet counts
- decreased blood levels of calcium, potassium, sodium, and magnesium
- increased creatine blood levels
- tiredness
- abnormalities in liver blood tests
- nausea
- rash
- loss of appetite
- COVID-19 infection
- headache

IBRANCE may cause fertility problems in males. This may affect your ability to father a child. Talk to your healthcare provider about family planning options before starting IBRANCE if this is a concern for you.

Tell your healthcare provider if you have any side effect that bothers you or that does not go away.

These are not all of the possible side effects of IBRANCE.

Call your doctor for medical advice about side effects. You may report side effects to FDA at 1-800-FDA-1088.

How should I store IBRANCE?

- Store IBRANCE at 68 °F to 77 °F (20 °C to 25 °C) in the original blister pack.

Keep IBRANCE and all medicines out of the reach of children.

General information about the safe and effective use of IBRANCE

Medicines are sometimes prescribed for purposes other than those listed in a Patient Information leaflet. Do not use IBRANCE for a condition for which it was not prescribed. Do not give IBRANCE to other people, even if they have the same symptoms you have. It may harm them. You can ask your pharmacist or healthcare provider for more information about IBRANCE that is written for health professionals.

What are the ingredients in IBRANCE?

Active ingredient: palbociclib

Inactive ingredients: microcrystalline cellulose, colloidal silicon dioxide, crospovidone, magnesium stearate, succinic acid, HPMC 2910/hypromellose, titanium dioxide, triacetin, and FD&C Blue #2/Indigo Carmine Aluminum Lake. In addition, the 75 mg and 125 mg tablets contain red iron oxide and the 100 mg tablets contain yellow iron oxide.

This product’s labeling may have been updated. For the most recent prescribing information, please visit www.pfizer.com.

LAB-1372-7.0

For more information, go to www.pfizer.com or call 1-800-438-1985.

This Patient Information has been approved by the U.S. Food and Drug Administration. Revised: September 2025

PRINCIPAL DISPLAY PANEL - 75 mg Tablet Dose Pack

PROFESSIONAL SAMPLE - NOT FOR SALE

Pfizer

NDC 63539-284-07

IBRANCE®
(palbociclib)

tablets

75 mg per tablet

This weekly pack contains:
7 tablets

Rx only

PRINCIPAL DISPLAY PANEL - 75 mg Tablet Dose Pack Box

PROFESSIONAL SAMPLE - NOT FOR SALE

Pfizer

NDC 63539-284-03

IBRANCE®
(palbociclib)

tablets

75 mg

21 tablets

Monthly Box Contains: 3 individual weekly
packs. Each pack contains 7 IBRANCE tablets
(75 mg per tablet).

Rx only

Safety
Label

PRINCIPAL DISPLAY PANEL - 100 mg Tablet Dose Pack

PROFESSIONAL SAMPLE - NOT FOR SALE

Pfizer

NDC 63539-486-07

IBRANCE®
(palbociclib)

tablets

100 mg per tablet

This weekly pack contains:
7 tablets

Rx only

PRINCIPAL DISPLAY PANEL - 100 mg Tablet Dose Pack Box

PROFESSIONAL SAMPLE - NOT FOR SALE

Pfizer

NDC 63539-486-03

IBRANCE®
(palbociclib)

tablets

100 mg

21 tablets

Monthly Box Contains: 3 individual weekly
packs. Each pack contains 7 IBRANCE tablets
(100 mg per tablet).

Rx only

Safety
Label

PRINCIPAL DISPLAY PANEL - 125 mg Tablet Dose Pack

PROFESSIONAL SAMPLE - NOT FOR SALE

Pfizer

NDC 63539-688-07

IBRANCE®
(palbociclib)

tablets

125 mg per tablet

This weekly pack contains:
7 tablets

Rx only

PRINCIPAL DISPLAY PANEL - 125 mg Tablet Dose Pack Box

PROFESSIONAL SAMPLE - NOT FOR SALE

Pfizer

NDC 63539-688-03

IBRANCE®
(palbociclib)

tablets

125 mg

21 tablets

Monthly Box Contains: 3 individual weekly
packs. Each pack contains 7 IBRANCE tablets
(125 mg per tablet).

Rx only

Safety
Label

PRINCIPAL DISPLAY PANEL - Topper Card

Your Monthly Box

Includes 3 weekly packs of
IBRANCE® (palbociclib) medication.

Fill in the dates below to help track your treatment cycle.

Treatment Cycle

Week 1 Week 2 Week 3
IBRANCE

Week 4
No IBRANCE

My Treatment Cycle Tracker

I start my Week 1
treatment cycle on:
________ / ______
MONTH DAY

After Week 4, I will start my
next treatment cycle on:
________ / ______
MONTH DAY

PAA119239